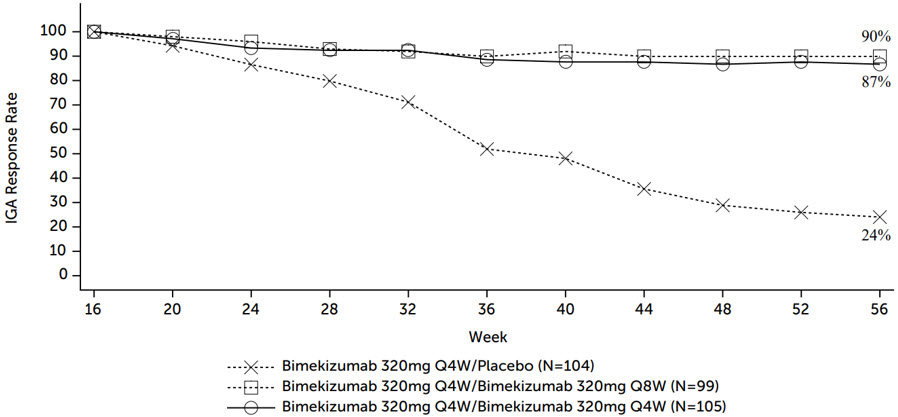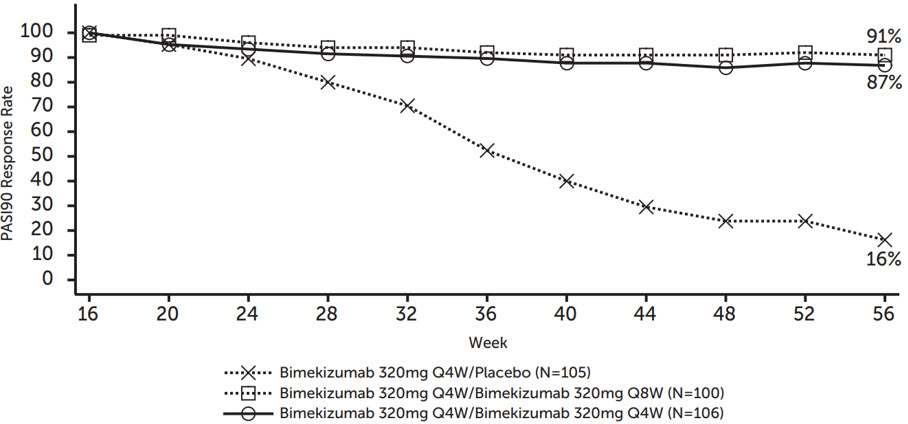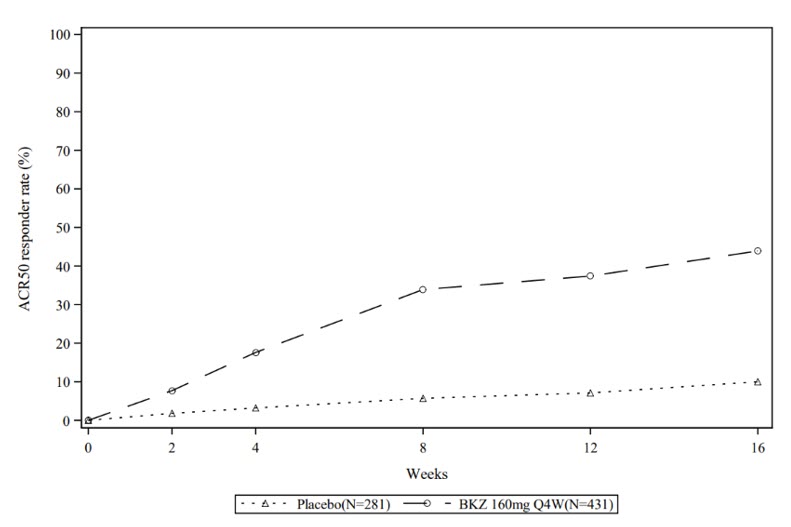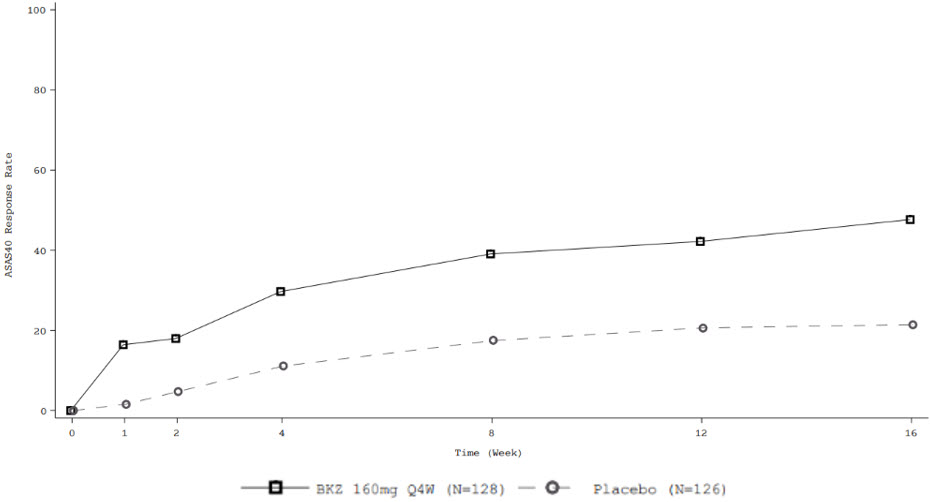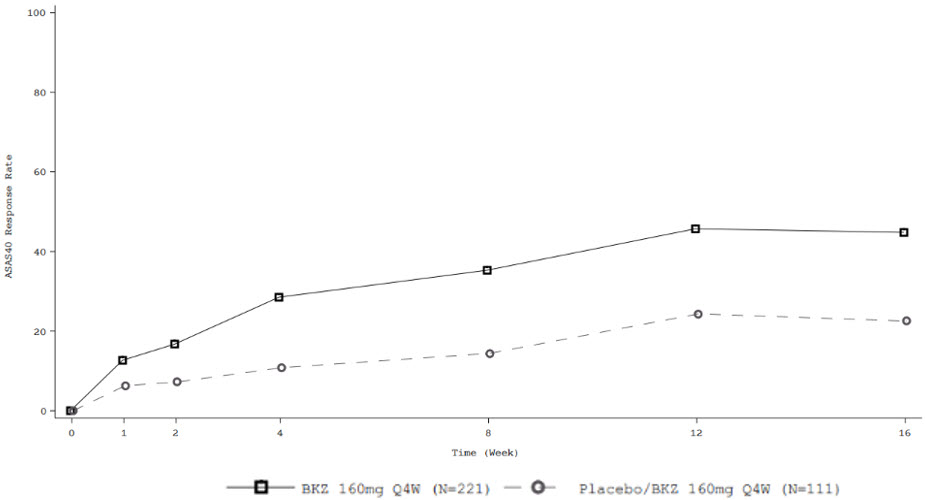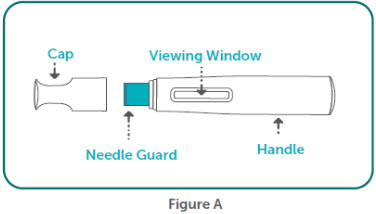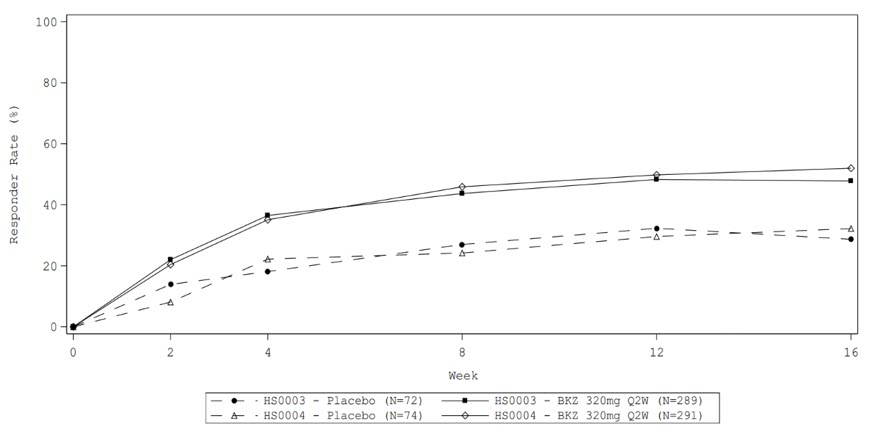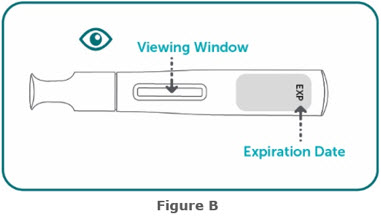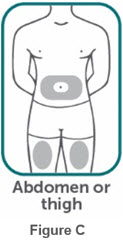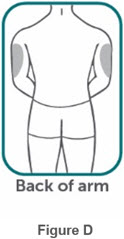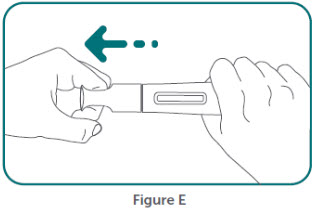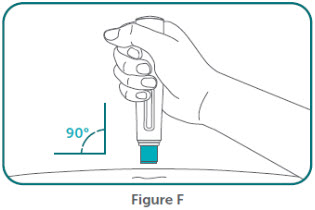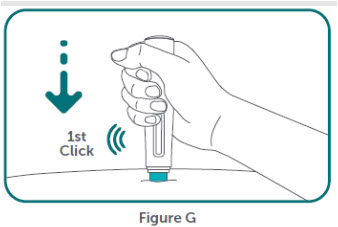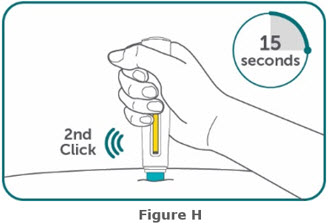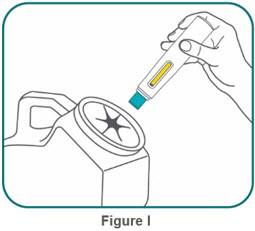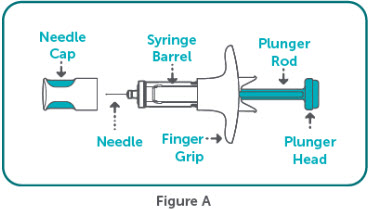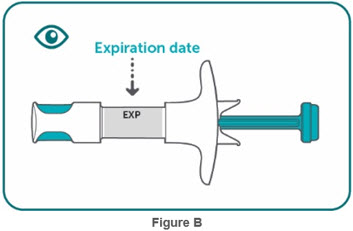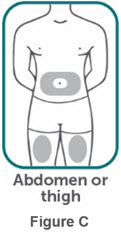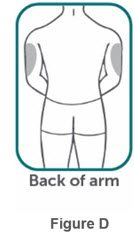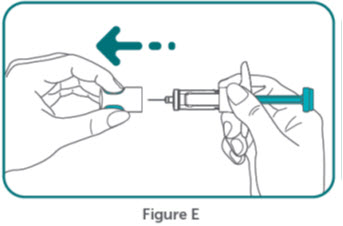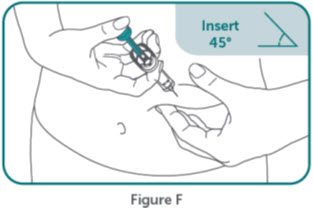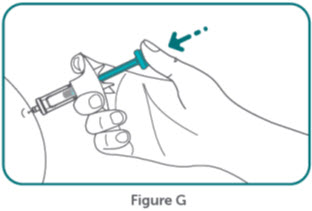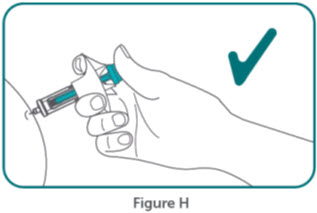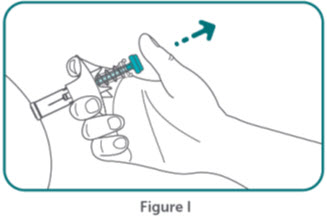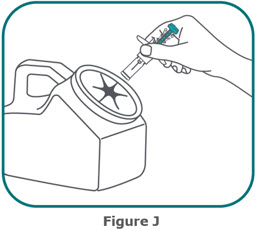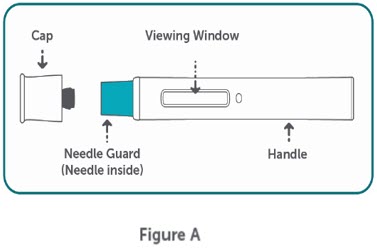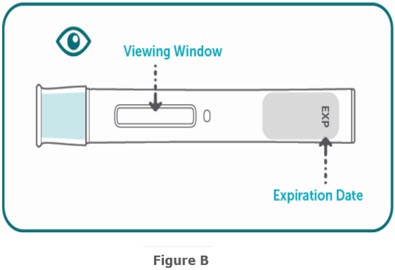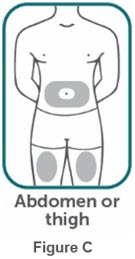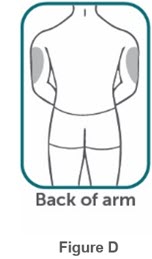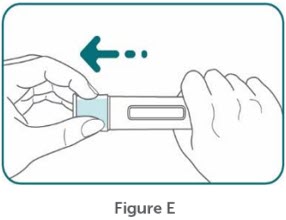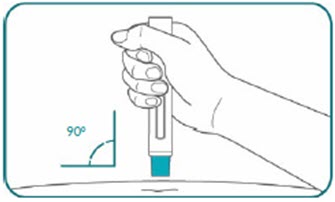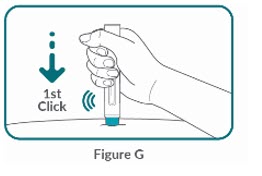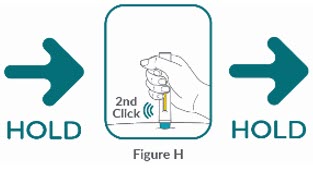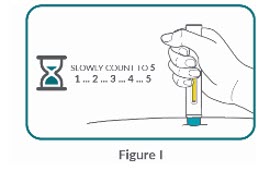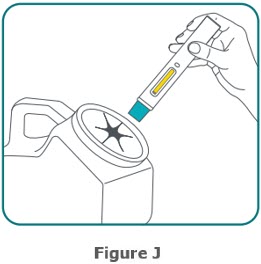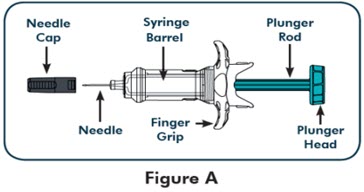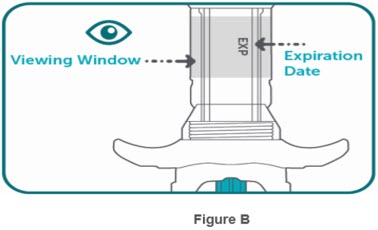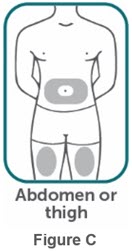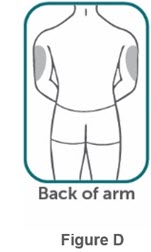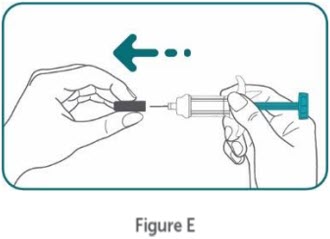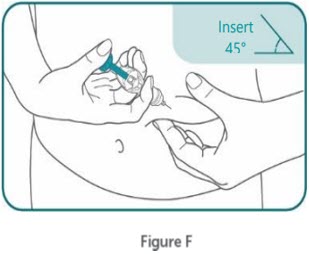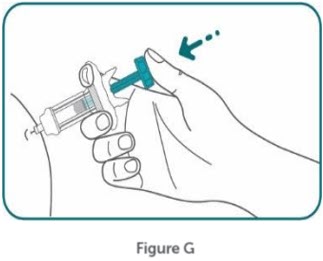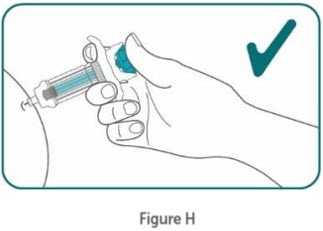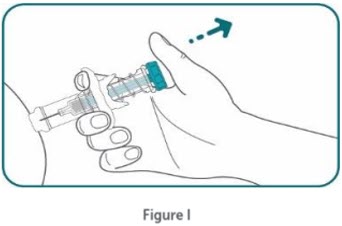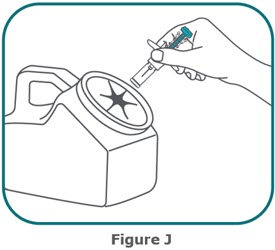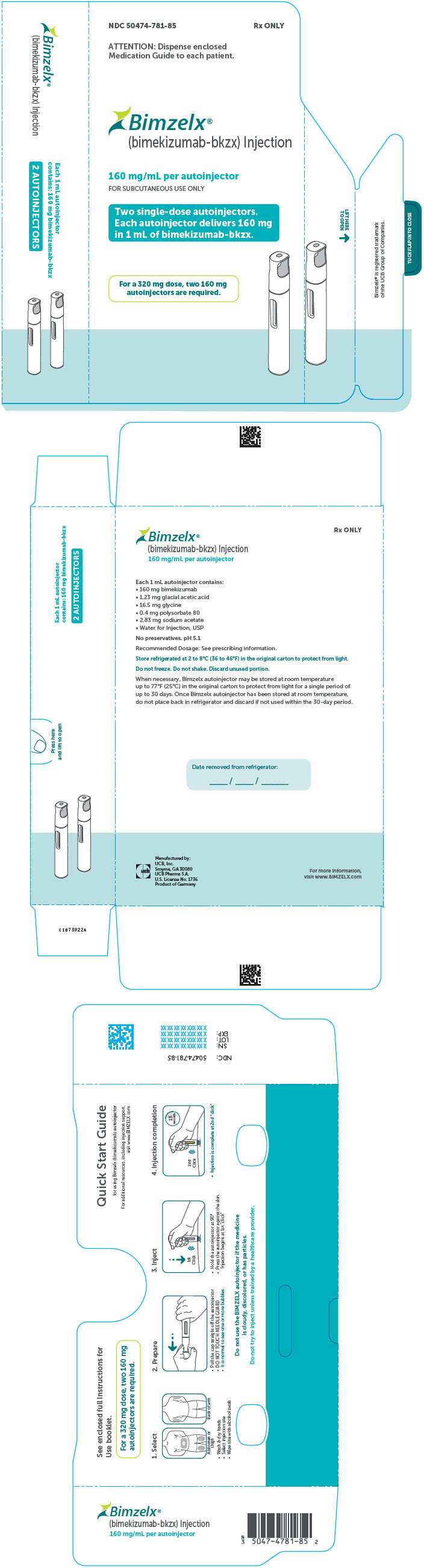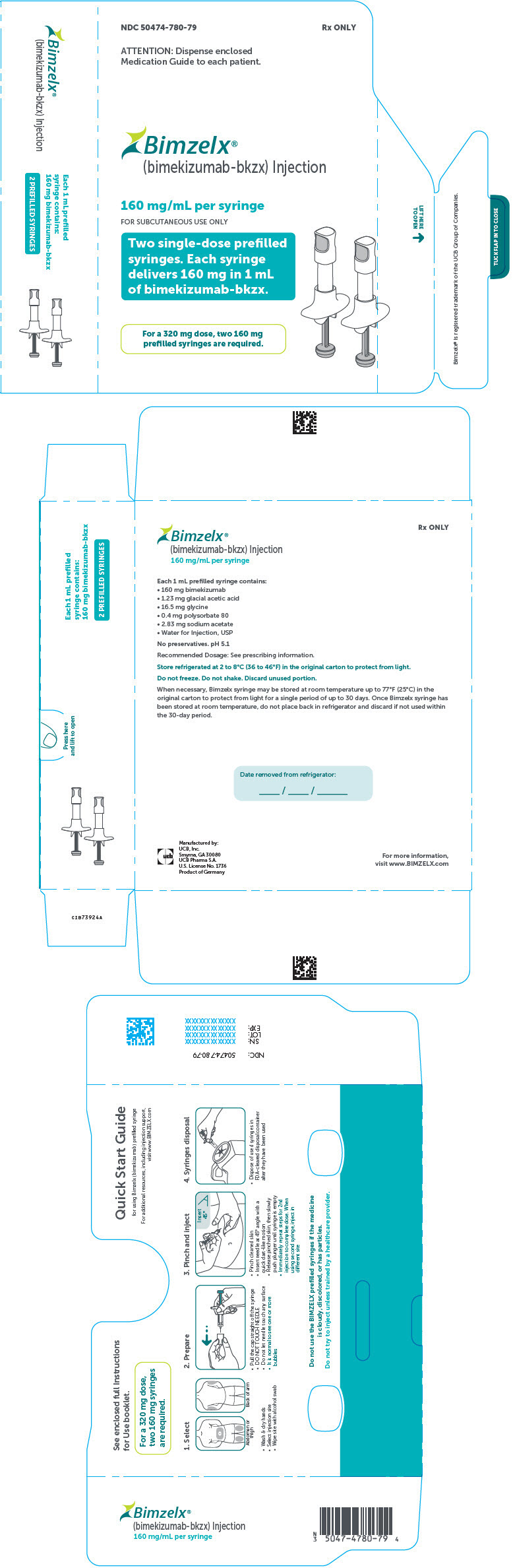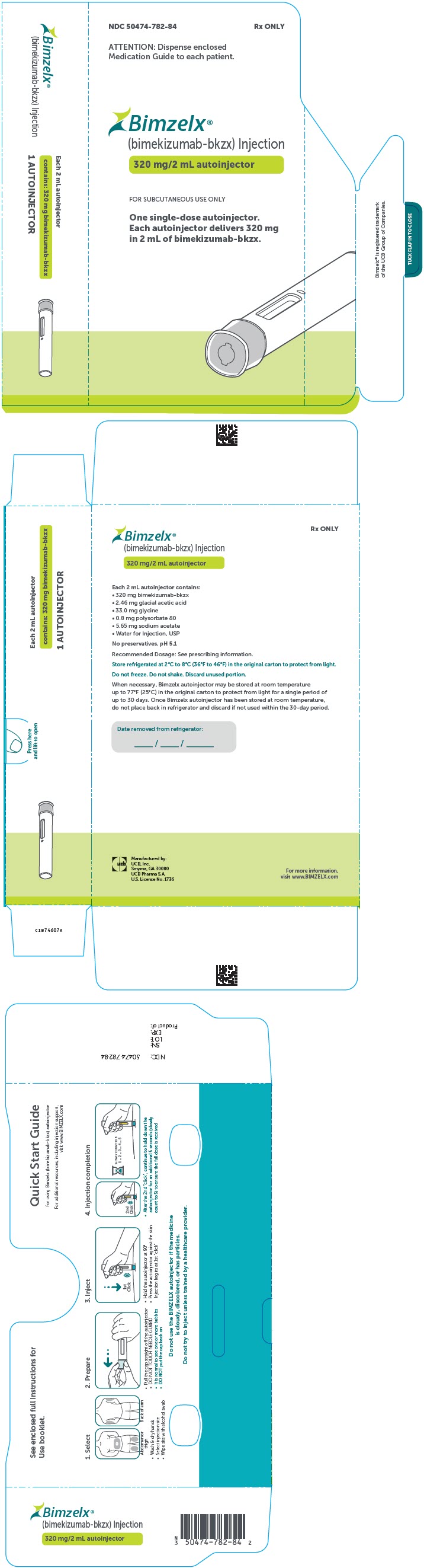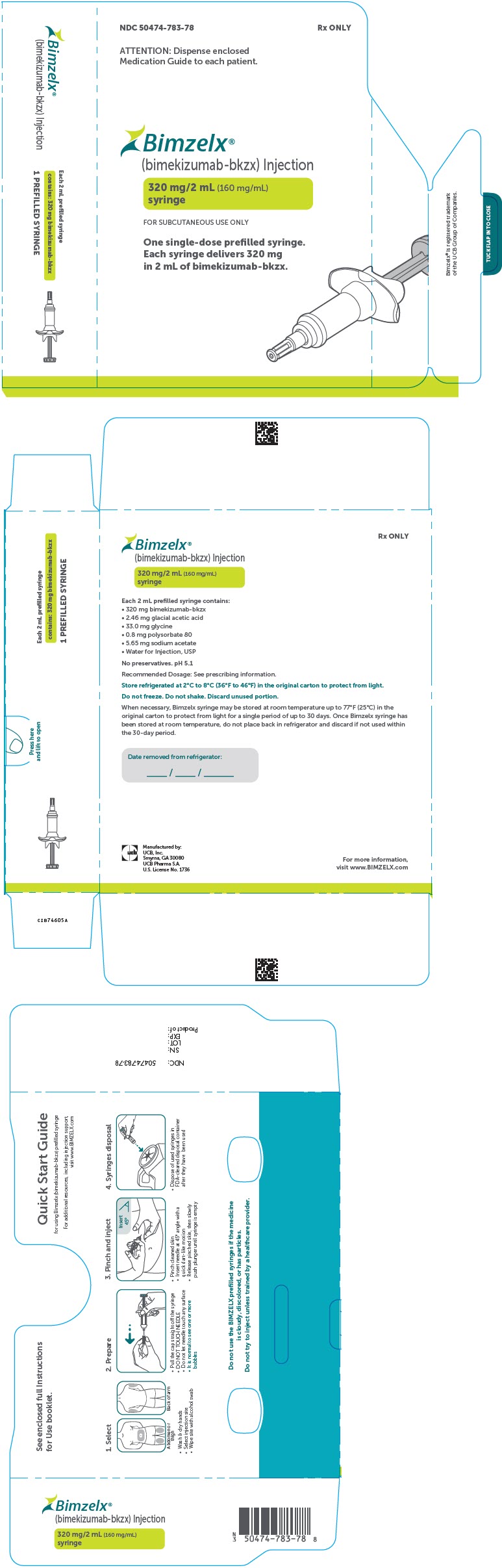 DRUG LABEL: Bimzelx
NDC: 50474-781 | Form: INJECTION, SOLUTION
Manufacturer: UCB, Inc.
Category: prescription | Type: HUMAN PRESCRIPTION DRUG LABEL
Date: 20250616

ACTIVE INGREDIENTS: BIMEKIZUMAB 160 mg/1 mL
INACTIVE INGREDIENTS: ACETIC ACID 1.23 mg/1 mL; GLYCINE 16.5 mg/1 mL; POLYSORBATE 80 0.4 mg/1 mL; SODIUM ACETATE 2.83 mg/1 mL; WATER

HIGHLIGHTS OF PRESCRIBING INFORMATION

These highlights do not include all the information needed to use BIMZELX safely and effectively. See full prescribing information for BIMZELX.
BIMZELX® (bimekizumab-bkzx) injection, for subcutaneous use
Initial U.S. Approval: 2023

RECENT MAJOR CHANGES

Indications and Usage (1.2, 1.3, 1.4, 1.5) | 11/2024
Dosage and Administration (2.3, 2.4, 2.5, 2.6, 2.7) | 11/2024
Warnings and Precautions (5.1, 5.2) | 11/2024

1 INDICATIONS AND USAGE

BIMZELX is a humanized interleukin-17A and F antagonist indicated for the treatment of:

- Moderate to severe plaque psoriasis (PSO)in adults who are candidates for systemic therapy or phototherapy. (1.1)
- Adults with active psoriatic arthritis (PsA). (1.2)
- Adults with active non-radiographic axial spondyloarthritis(nr-axSpA) with objective signs of inflammation. (1.3)
- Adults with active ankylosing spondylitis(AS). (1.4)
- Adults with moderate to severe hidradenitis suppurativa (HS). (1.5)

2 DOSAGE AND ADMINISTRATION

- Prior to treatment: (2.1)
  - Evaluate patients for tuberculosis infection.
  - Test liver enzymes, alkaline phosphatase, and bilirubin.
  - Complete all age-appropriate vaccinations as recommended by current immunization guidelines.
- Plaque Psoriasis
  - Administer 320 mg by subcutaneous injection at Weeks 0, 4, 8, 12, and 16, then every 8 weeks thereafter. For patients weighing 120 kg or more, consider a dose of 320 mg every 4 weeks after Week 16. (2.2)
- Psoriatic Arthritis
  - Administer 160 mg by subcutaneous injection every 4 weeks. (2.3)
  - For patients with coexisting moderate to severe plaque psoriasis, use the dosage and administration for plaque psoriasis. (2.2)
- Non-Radiographic Axial Spondyloarthritis
  - Administer 160 mg by subcutaneous injection every 4 weeks. (2.4)
- Ankylosing Spondylitis
  - Administer 160 mg by subcutaneous injection every 4 weeks. (2.5)
- Hidradenitis Suppurativa
  - Administer 320 mg by subcutaneous injection at Week 0, 2, 4, 6, 8, 10, 12, 14 and 16, then every 4 weeks thereafter. (2.6)
- See full prescribing information for recommendations regarding missed doses, preparation and administration instructions. (2.7, 2.8, 2.9)

3 DOSAGE FORMS AND STRENGTHS

- Injection: 160 mg/mL in a single-dose prefilled syringe or single-dose prefilled autoinjector. (3)
- Injection: 320 mg/2 mL (160 mg/mL) in a single-dose prefilled syringe or single-dose prefilled autoinjector. (3)

4 CONTRAINDICATIONS

None. (4)

5 WARNINGS AND PRECAUTIONS

- Suicidal Ideation and Behavior (SI/B): May increase risk of SI/B. Advise patients, their caregivers, and families to monitor for the emergence or worsening of depression, suicidal ideation, or other mood changes. If such changes occur, instruct patients to promptly seek medical attention or call the National Suicide and Crisis Lifeline at 988. Carefully weigh risks and benefits of treatment with BIMZELX in patients with a history of severe depression and/or suicidal ideation or behavior. (5.1)
- Infections: May increase risk of infection. Instruct patients to seek medical advice if signs or symptoms of clinically important infection occur. If such an infection develops, do not administer BIMZELX until the infection resolves. (5.2)
- Tuberculosis (TB): Avoid use in patients with active TB. Initiate treatment of latent TB prior to BIMZELX treatment. (5.3)
- Liver Biochemical Abnormalities: Elevated serum transaminases were reported in clinical trials. Test liver enzymes, alkaline phosphatase, and bilirubin at baseline and according to routine patient management. Permanently discontinue use of BIMZELX in patients with causally - associated combined elevations of transaminases and bilirubin. (5.4)
- Inflammatory Bowel Disease (IBD): Cases of IBD were reported in clinical trials with IL-17 inhibitors, including BIMZELX. Avoid use of BIMZELX in patients with active IBD. Monitor patients for signs and symptoms of IBD and discontinue treatment if new onset or worsening of signs and symptoms occurs. (5.5)
- Immunizations: Avoid the use of live vaccines in patients treated with BIMZELX. (5.6)

6 ADVERSE REACTIONS

Most common adverse reactions are:

- Psoriasis and Hidradenitis Suppurativa(incidence ≥ 1%): upper respiratory tract infections, oral candidiasis, headache, injection site reactions, tinea infections, gastroenteritis, Herpes simplex infections, acne, folliculitis, other candida infections, and fatigue. (6.1)
- Psoriatic Arthritis(incidence ≥ 2%): upper respiratory tract infections, oral candidiasis, headache, diarrhea, and urinary tract infection. (6.1)
- Non-Radiographic Axial Spondyloarthritis(incidence ≥ 2%): upper respiratory tract infections, oral candidiasis, headache, diarrhea, cough, fatigue, musculoskeletal pain, myalgia, tonsilitis, transaminase increase, and urinary tract infection. (6.1)
- Ankylosing Spondylitis(incidence ≥ 2%): upper respiratory tract infections, oral candidiasis, headache, diarrhea, injection site pain, rash and vulvovaginal mycotic infection. (6.1)

To report SUSPECTED ADVERSE REACTIONS, contact UCB, Inc. at 844-599-2273 or FDA at 1-800-FDA-1088 or www.fda.gov/medwatch.

FULL PRESCRIBING INFORMATION

1 INDICATIONS AND USAGE

1.1 Plaque Psoriasis

BIMZELX is indicated for the treatment of moderate to severe plaque psoriasis in adults who are candidates for systemic therapy or phototherapy.

1.2 Psoriatic Arthritis

BIMZELX is indicated for the treatment of adults with active psoriatic arthritis.

1.3 Non-Radiographic Axial Spondyloarthritis

BIMZELX is indicated for the treatment of adults with active non-radiographic axial spondyloarthritis with objective signs of inflammation.

1.4 Ankylosing Spondylitis

BIMZELX is indicated for the treatment of adults with active ankylosing spondylitis.

1.5 Hidradenitis Suppurativa

BIMZELX is indicated for the treatment of adults with moderate to severe hidradenitis suppurativa.

2 DOSAGE AND ADMINISTRATION

2.1 Recommended Evaluations and Immunization Prior to Treatment Initiation

- Evaluate patients for tuberculosis (TB) infection prior to initiating treatment with BIMZELX [see Warnings and Precautions (5.3)] .
- Test liver enzymes, alkaline phosphatase and bilirubin prior to initiating treatment with BIMZELX [see Warnings and Precautions (5.4)] .
- Complete all age-appropriate vaccinations as recommended by current immunization guidelines [see Warning and Precautions (5.6)] .

2.2 Recommended Dosage for Plaque Psoriasis

The recommended dosage is 320 mg by subcutaneous injection at Weeks 0, 4, 8, 12, and 16, then every 8 weeks thereafter .For patients weighing 120 kg or more, consider a dosage of 320 mg every 4 weeks after Week 16 [see Clinical Pharmacology (12.3)] .

2.3 Recommended Dosage for Psoriatic Arthritis

The recommended dosage is 160 mg by subcutaneous injection every 4 weeks.

For psoriatic arthritis patients with coexistent moderate to severe plaque psoriasis, use the dosing regimen for adult patients with plaque psoriasis [see Dosage and Administration (2.2)] .

2.4 Recommended Dosage for Non-Radiographic Axial Spondyloarthritis

The recommended dosage is 160 mg by subcutaneous injection every 4 weeks.

2.5 Recommended Dosage for Ankylosing Spondylitis

The recommended dosage is 160 mg by subcutaneous injection every 4 weeks.

2.6 Recommended Dosage for Hidradenitis Suppurativa

The recommended dosage is 320 mg by subcutaneous injection at Weeks 0, 2, 4, 6, 8, 10, 12, 14, and 16, then every 4 weeks thereafter.

2.7 Missed Doses

If a dose is missed, administer the dose as soon as possible. Thereafter, resume dosing at the regularly scheduled interval.

2.8 Preparation Instructions

- Before injecting, remove the carton with BIMZELX from the refrigerator and allow BIMZELX to reach room temperature (30 to 45 minutes) without removing the prefilled syringes or autoinjectors from the carton to protect from light.
- Inspect visually for particulate matter and discoloration prior to administration, whenever solution and container permit. BIMZELX injection is clear to slightly opalescent, and colorless to pale brownish- yellow. Do not use if the solution contains visible particles, is discolored or cloudy.

2.9 Administration Instructions

- BIMZELX is intended for use under the guidance and supervision of a healthcare professional. Patients may self-inject after training in subcutaneous injection technique. Provide proper training to patients and/or caregivers on the subcutaneous injection technique of BIMZELX according to the "Instructions for Use" [see Instructions for Use].
- If two separate 160 mg injections are used to achieve the recommended dose, administer each injection subcutaneously at a different anatomic location (such as thighs, abdomen or back of upper arm). Discard the syringes or autoinjectors after use. Do not reuse.
- Do not inject BIMZELX within 2 inches (5 cm) of the navel or into areas where the skin is tender, bruised, red, hard, thick, scaly, or affected by psoriasis. Administration of BIMZELX in the upper, outer arm may only be performed by a healthcare professional or caregiver. Rotate the injection site with each injection.

3 DOSAGE FORMS AND STRENGTHS

- Injection (1 mL): 160 mg/mL clear to slightly opalescent, and colorless to pale brownish-yellow solution in a single-dose prefilled syringe or single-dose prefilled autoinjector.
- Injection (2 mL): 320 mg/2 mL (160 mg/mL) clear to slightly opalescent, and colorless to pale brownish-yellow solution in a single-dose prefilled syringe or single-dose prefilled autoinjector.

4 CONTRAINDICATIONS

None.

5 WARNINGS AND PRECAUTIONS

5.1 Suicidal Ideation and Behavior

An increased incidence of new onset or worsening suicidal ideation and behavior was observed in subjects treated with BIMZELX. A causal association between treatment with BIMZELX and increased risk of suicidal ideation and behavior has not been definitively established.

Suicidal ideation and behavior were prospectively monitored using the Columbia Suicide Severity Rating Scale (C-SSRS) in clinical trials. The C-SSRS is an interview-based instrument used to monitor for the presence and severity of suicidal ideation (ranging from "none" to "active suicidal ideation with specific plan and intent") and behaviors (rating the injury and potential lethality of self-injury, if present).

Plaque Psoriasis

During the two 16-week, placebo-controlled periods of Trials Ps-1 and Ps-2, higher rates of suicidal ideation as assessed by C-SSRS were reported in BIMZELX-treated subjects than in subjects receiving placebo. Pooled analysis of C-SSRS data indicated that 12/670 (1.8%) BIMZELX-treated subjects and 1/169 (0.6%) subjects receiving placebo reported passive suicidal ideation with an estimated relative risk of 3.0 (95% confidence interval: 0.39, 22.74). Subjects without a prior history of SI/B treated with BIMZELX also reported a higher rate of new onset suicidal ideation on the C-SSRS than subjects receiving placebo (1.3% vs 0.6%). During the open-label extension trial, one completed suicide was reported in a BIMZELX-treated subject [see Adverse Reactions (6.1)].

Psoriatic Arthritis

Pooled analysis of C-SSRS data from the two 16-week, placebo-controlled periods of Trials PsA-1 and PsA-2 indicated that 2/698 (0.3%) BIMZELX-treated subjects and 3/413 (0.7%) subjects receiving placebo reported passive suicidal ideation with an estimated relative risk of 0.35 (95% confidence interval: 0.05, 2.29) [see Adverse Reactions (6.1)] .

Non-Radiographic Axial Spondyloarthritis

Analysis of C-SSRS data from a 16-week, placebo-controlled period of Trial nr-axSpA-1 indicated that no subjects, being treated either with BIMZELX or placebo, reported suicidal ideation [see Adverse Reactions (6.1)] .

Ankylosing Spondylitis

Analysis of C-SSRS data from a 16-week, placebo-controlled period of Trial AS-1 indicated that no subjects, being treated either with BIMZELX or placebo, reported suicidal ideation [see Adverse Reactions (6.1)] .

Hidradenitis Suppurativa

During the two 16-week, placebo-controlled periods of Trials HS-1 and HS-2, higher rates of suicidal ideation as assessed by C-SSRS were reported in BIMZELX-treated subjects than in subjects receiving placebo. Based on a pooled analysis of the first 16 weeks of the placebo controlled clinical trials, 16/861 subjects in the BIMZELX group (1.9 %) reported suicidal ideation on the C-SSRS compared to 1/146 subjects in the placebo group (0.7%) with an estimated relative risk of 2.70 (95% confidence interval: 0.36, 20.12). Subjects without a prior history of SI/B treated with BIMZELX also reported a higher rate of new-onset suicidal ideation on the C-SSRS than subjects treated with placebo (0.9% vs. 0%). [see Adverse Reactions 6.1].

Consider the potential risks and benefits before prescribing BIMZELX to patients with a history of severe depression or suicidal ideation or behavior. Advise patients, their caregivers, and families to monitor for the emergence or worsening of depression, suicidal ideation, or other mood changes. If such changes occur, instruct patients to promptly seek medical attention or call the National Suicide and Crisis Lifeline at 988 [see Patient Counseling Information (17)] . Refer BIMZELX-treated patients with new or worsening symptoms of depression or suicidal ideation and/or behavior to a mental health professional, as appropriate. Re-evaluate the risks and benefits of continuing treatment with BIMZELX if such events occur.

5.2 Infections

BIMZELX may increase the risk of infections, including serious infections.

Do not initiate treatment with BIMZELX in patients with any clinically important active infection until the infection resolves or is adequately treated.

In patients with a chronic infection or a history of recurrent infection, consider the risks and benefits prior to prescribing BIMZELX. Instruct patients to seek medical advice if signs or symptoms of clinically important infection occur. If a patient develops such an infection or is not responding to standard therapy, monitor the patient closely and discontinue BIMZELX until the infection resolves.

5.3 Tuberculosis

Evaluate patients for tuberculosis (TB) infection prior to initiating treatment with BIMZELX. Avoid the use of BIMZELX in patients with active TB infection. Initiate treatment of latent TB prior to administering BIMZELX. Consider anti-TB therapy prior to initiation of BIMZELX in patients with a past history of latent or active TB in whom an adequate course of treatment cannot be confirmed. Closely monitor patients treated with BIMZELX for signs and symptoms of active TB during and after treatment.

5.4 Liver Biochemical Abnormalities

Treatment with BIMZELX was associated with increased incidence of liver enzyme elevations compared to treatment with placebo in randomized clinical trials. Liver serum transaminase elevations > 3 times the upper limit of normal were reported in subjects treated with BIMZELX [see Adverse Reactions (6.1)] . Elevated liver serum transaminases resolved after discontinuation of BIMZELX.

Test liver enzymes, alkaline phosphatase, and bilirubin at baseline, periodically during treatment with BIMZELX and according to routine patient management. If treatment-related increases in liver enzymes occur and drug-induced liver injury is suspected, interrupt BIMZELX until a diagnosis of liver injury is excluded. Permanently discontinue BIMZELX in patients with causally associated combined elevations of transaminases and bilirubin. Patients with acute liver disease or cirrhosis may be at increased risk for severe hepatic injury; avoid use of BIMZELX in these patients.

5.5 Inflammatory Bowel Disease

Cases of inflammatory bowel disease (IBD) have been reported in patients treated with IL-17 inhibitors, including BIMZELX [see Adverse Reactions (6.1)]. Avoid use of BIMZELX in patients with active IBD. During BIMZELX treatment, monitor patients for signs and symptoms of IBD and discontinue treatment if new onset or worsening of signs and symptoms occurs.

5.6 Immunizations

Prior to initiating therapy with BIMZELX, complete all age-appropriate vaccinations according to current immunization guidelines. Avoid the use of live vaccines in patients treated with BIMZELX. Limited data are available regarding coadministration of BIMZELX with non-live vaccines [see Clinical Pharmacology (12.2)] .

6 ADVERSE REACTIONS

The following adverse reactions have been observed with BIMZELX and are discussed in greater detail in other sections of the labeling:

- Suicidal Ideation and Behavior [see Warnings and Precautions (5.1)]
- Infections [see Warnings and Precautions (5.2)]
- Liver Biochemical Abnormalities [see Warnings and Precautions (5.4)]
- Inflammatory Bowel Disease [see Warnings and Precautions (5.5)]

6.1 Clinical Trials Experience

Because clinical trials are conducted under widely varying conditions, adverse reaction rates observed in the clinical trials of a drug cannot be directly compared to rates in the clinical trials of another drug and may not reflect the rates observed in practice.

Plaque Psoriasis Clinical Trials

In clinical trials, a total of 1,789 subjects with plaque psoriasis were treated with BIMZELX. Of these, 1,073 subjects were exposed to BIMZELX for at least one year.

The safety of BIMZELX was evaluated in two placebo-controlled trials (Ps-1 and Ps-2), an active-controlled trial (Ps-3), and an open-label extension trial. Data from Trials Ps-1 and Ps-2 in 839 subjects (mean age 45 years, 72% male, 84% White) were pooled to evaluate the safety of BIMZELX in comparison to placebo up to 16 weeks after treatment initiation. A total of 670 subjects were treated during this initial period with BIMZELX 320 mg at Weeks 0, 4, 8, 12, and 16. Table 1 summarizes the adverse reactions that occurred at a rate of 1% or greater and at a higher rate in the BIMZELX group than the placebo group.

Table 1: Adverse Reactions Occurring in ≥1% of Subjects with Plaque Psoriasis in the BIMZELX Group and More Frequently than in the Placebo Group in Trials Ps-1 and Ps-2
 | BIMZELX N=670 n (%) | Placebo N=169 n (%)
URI [Upper Respiratory Infections include nasopharyngitis, upper respiratory tract infection, pharyngitis, rhinitis, viral upper respiratory tract infection, tonsillitis, sinusitis, pharyngitis streptococcal, pharyngitis bacterial, peritonsillar abscess, viral rhinitis, and influenza] | 102 (15) | 24 (14)
Oral Candidiasis [Oral Candidiasis includes oral candidiasis, oropharyngeal candidiasis, oral fungal infection, fungal pharyngitis, and oropharyngitis fungal] | 61 (9) | 0 (0)
Headache | 22 (3) | 0 (0)
Injection Site Reactions [Injection Site Reactions include injection site reaction, injection site erythema, injection site pain, injection site edema, injection site bruising, and injection site swelling] | 19 (3) | 2 (1)
Tinea Infections [Tinea Infections include tinea pedis, fungal skin infection, tinea versicolor, tinea cruris, tinea infection, body tinea, and onychomycosis] | 18 (3) | 1 (1)
Gastroenteritis [Gastroenteritis includes Enterovirus infection, gastroenteritis, gastroenteritis bacterial, and gastroenteritis viral] | 12 (2) | 0 (0)
Herpes Simplex Infections [Herpes Simplex Infections include herpes simplex and oral herpes] | 9 (1) | 0 (0)
Acne | 8 (1) | 0 (0)
Folliculitis | 8 (1) | 0 (0)
Other Candida Infections [Other Candida Infections include vulvovaginal candidiasis, vulvovaginal mycotic infection, skin candida, and genital candidiasis.] | 7 (1) | 1 (1)
Fatigue | 7 (1) | 0 (0)

Adverse reactions that occurred in < 1% but > 0.1% of subjects in the BIMZELX group and at a higher rate than in the placebo group through Week 16 were neutropenia, eczema, otitis externa, otitis media, and pyrexia.

The safety of BIMZELX was evaluated in another active-controlled trial (Ps-4) in 743 adult subjects who received BIMZELX 320 mg every 4 weeks or every 8 weeks through Week 48.

Specific Adverse Reactions

Suicidal Ideation and Behavior:The study populations of Trial Ps-1, Trial Ps-2, Trial Ps-3 and Trial Ps-4 excluded subjects with active suicidal ideation, suicidal ideation within the month prior to screening, a history of suicide attempt within the past 5 years prior to screening, or moderately severe to severe major depression (i.e., score of ≥15 on the screening Patient Health Questionnaire-9 (PHQ-9)).

Analysis of pooled C-SSRS data from the first 16 weeks of placebo-controlled clinical trials indicated that 12/670 (1.8%) BIMZELX-treated subjects and 1/169 (0.6%) subjects receiving placebo reported passive suicidal ideation with an estimated relative risk of 3.0 (95% confidence interval: 0.39, 22.74). Subjects without a prior history of SI/B treated with BIMZELX also reported a higher rate of new onset suicidal ideation on the C-SSRS than subjects receiving placebo (1.3% vs 0.6%).

During the course of the clinical trials for plaque psoriasis, there was 1 completed suicide in the open label extension trial after 718 days of treatment (1/2,480; 0.01/100 patient-years). The completed suicide was reported in a subject without a past reported psychiatric history. There were also 3 suicide attempts (3/2,480; 0.04/100 patient-years); 2 of these subjects had a history of prior suicide attempts.

Infections: During the placebo-controlled period of Trials Ps-1 and Ps-2, infections were reported in 36% of subjects (141.7 per 100 patient-years) treated with BIMZELX compared with 23% of subjects (84.6 per 100 patient-years) receiving placebo. Serious infections occurred in 0.3% of subjects (1.0 per 100 patient-years) treated with BIMZELX and 0% subjects receiving placebo .

The most common infections were upper respiratory tract infections and Candida infections, including oral candidiasis (oral candidiasis, oropharyngeal candidiasis, oral fungal infection, fungal pharyngitis, and oropharyngitis fungal) occurring in 9% (30.6 per 100 patient-years) of subjects treated with BIMZELX and other Candida infections (vulvovaginal candidiasis, vulvovaginal mycotic infection, skin candida, and genital candidiasis) in 1% (3.4 per 100 patient-years) of subjects treated with BIMZELX compared to 0% and 1%, respectively, of subjects receiving placebo.

During the combined initial, maintenance, and open-label extension treatment periods of trials Ps-1, Ps-2, Ps-3, and the open-label extension trial, infections were reported in 63% of subjects treated with BIMZELX (120.4 per 100 patient-years). Serious infections were reported in 1.5% of subjects treated with BIMZELX (1.6 per 100 patient-years).

Inflammatory Bowel Disease:In clinical trials in subjects with plaque psoriasis, subjects with active inflammatory bowel disease were excluded. In these trials, which included 2,480 subjects exposed to BIMZELX accounting for 5,830 patient-years, adjudicated cases of new onset of inflammatory bowel disease (including ulcerative colitis (UC), Crohn's disease (CD) and IBD-undetermined) occurred in seven subjects (0.12 per 100 patient-years); the majority of these cases were serious and resulted in discontinuation of therapy.

Liver Biochemical Abnormalities:During the placebo-controlled period of Trials Ps-1 and Ps-2, liver serum transaminase elevations (> 3 times the upper limit of normal [ULN]) occurred in 1.0% of subjects treated with BIMZELX versus 0.6% of subjects receiving placebo. The time to onset of these adverse reactions varied between 28 and 198 days after starting BIMZELX treatment. Elevated liver serum transaminases resolved during continued treatment or after discontinuation of BIMZELX.

Safety through Week 56

During the maintenance period (Week 16 through Week 52 of Trial Ps-1 and Week 56 of Trial Ps-2), adverse reactions were consistent with those observed during the initial 16 weeks of treatment with BIMZELX. During the maintenance treatment periods of Trial Ps-2 and Trial Ps-3, the rates of adverse reactions were similar between subjects treated with BIMZELX 320 mg every four week and every eight weeks, after the initial 16 weeks of treatment.

Safety through Week 128

During the open-label extension trial, including data from Week 56 through Week 128, new adverse reactions of suicide attempt and a completed suicide occurred [described above in Suicidal Ideation and Behavior].

Additional Safety Data

In an active-controlled clinical trial (Trial Ps-4), 691 subjects with plaque psoriasis were treated with BIMZELX for up to 144 weeks. Adverse reactions were consistent with those observed during the initial 16 weeks of treatment and with the overall safety profile of BIMZELX.

Psoriatic Arthritis Clinical Trials

The safety of BIMZELX was evaluated in two placebo-controlled trials (PsA-1 and PsA-2). Data from Trials PsA-1 and PsA-2 in 1,111 subjects (mean age 49 years, 47% male, 96% White) were pooled to evaluate the safety of BIMZELX in comparison to placebo up to 16 weeks after treatment initiation. A total of 698 subjects were treated during this initial period with BIMZELX 160 mg at Weeks 0, 4, 8, 12, and 16. Table 2 summarizes the adverse reactions that occurred at a rate of 2% or greater and at a higher rate in the BIMZELX group than the placebo group.

Table 2: Adverse Reactions Occurring in ≥2% of Subjects with Psoriatic Arthritis in the BIMZELX Group and More Frequently than in the Placebo Group in Trials PsA-1 and PsA-2
 | BIMZELX N=698 n (%) | Placebo N=413 n (%)
URI [Upper Respiratory Tract Infections (URI) includes: nasopharyngitis, upper respiratory tract infection, pharyngitis, sinusitis, and rhinitis.] | 99 (14) | 41 (10)
Headache | 25 (4) | 7 (2)
Diarrhea | 19 (3) | 8 (2)
Urinary Tract Infection | 14 (2) | 7 (2)
Oral Candidiasis | 16 (2) | 0

Adverse reactions that occurred in < 2% but > 1% of subjects in the BIMZELX group and at a higher rate than in the placebo group through Week 16 included neutropenia (placebo: n=0; BIMZELX: n=8 (1.1%)), stomatitis (placebo: n=0; BIMZELX: n=8 (1.1%)), bronchitis (placebo: n=1 (0.2%); BIMZELX: n=11 (1.6%)), and oropharyngeal pain (placebo: n=0; BIMZELX: n=9 (1.3%)).

Specific Adverse Reactions

Suicidal Ideation and Behavior:The neuropsychiatric inclusion/exclusion criteria in PsA trials were the same as in PSO.

Based on a pooled analysis of the first 16 weeks of the placebo controlled clinical trials, 2 of the 698 subjects in the BIMZELX group (0.3%) reported passive suicidal ideation on the C-SSRS compared to 3 of 413 subjects in the placebo group (0.7%).

During the entire clinical trial program for PsA (2,664 patient-years), there were 2 cases of suicidal ideation (2/1413; 0.08/100 patient-years) and 1 suicide attempt (1/1413; 0.04/100 patient-years); all reported in BIMZELX-treated subjects with pre-existing psychiatric conditions.

Infections:During the placebo-controlled period of Trials PsA-1 and PsA-2, infections were reported in 27% of subjects (100.7 per 100 patient-years) treated with BIMZELX compared with 18% of subjects (62.8 per 100 patient-years) treated with placebo. Serious infections occurred in 0.4% of subjects (1.4 per 100 patient-years) treated with BIMZELX and 0% treated with placebo .

The most common infections were upper respiratory tract infections, nasopharyngitis, urinary tract infection and Candida infections, including oral candidiasis (oral candidiasis, oral fungal infection, and tongue fungal infection), occurring in 3.2% (10.2 per 100 patient-years) of subjects treated with BIMZELX and other Candida infections (skin candida, vulvovaginal candidiasis, and vulvovaginal mycotic infection) in 0.6% (1.8 per 100 patient-years) of subjects treated with BIMZELX compared to 0% and 1%, respectively, of subjects treated with placebo.

During the combined placebo-controlled, maintenance and open-label extension treatment periods of Trials PsA-1 and PsA-2, infections were reported in 58% of subjects treated with BIMZELX (58.5 per 100 patients-years). Serious infections were reported in 2% of subjects treated with BIMZELX (1.3 per 100 patient-years).

Inflammatory Bowel Disease:In clinical trials in subjects with psoriatic arthritis, subjects with active inflammatory bowel disease were excluded. In these trials, which included 1,413 subjects exposed to BIMZELX accounting for 2,664 patient-years, adjudicated cases of new onset of inflammatory bowel disease (including ulcerative colitis (UC) and IBD) occurred in 2 subjects (0.08 per 100 patient-years); one of these cases was serious and none resulted in discontinuation of therapy.

Liver Biochemical Abnormalities:During the placebo-controlled period of Trials PsA-1 and PsA-2, liver serum transaminase elevations (> 3 times the upper limit of normal [ULN]) occurred in 1.3% of subjects treated with BIMZELX versus 0% of subjects receiving placebo. Elevated liver serum transaminases resolved during continued treatment or after discontinuation of BIMZELX.

Safety through Week 52

During the maintenance period (Week 16 through Week 52 of Trial PsA-1), adverse reactions were consistent with those observed during the initial 16 weeks of treatment and with the overall safety profile of BIMZELX.

Non-Radiographic Axial Spondyloarthritis Clinical Trials

BIMZELX was evaluated in a placebo-controlled trial (Trial nr-axSpA-1) in subjects with non-radiographic axial spondyloarthritis (128 subjects on BIMZELX and 126 subjects on placebo). The safety profile observed in subjects with non-radiographic axial spondyloarthritis treated with BIMZELX was overall similar to the safety profile seen in subjects with psoriatic arthritis, except for cough, musculoskeletal pain, myalgia, tonsilitis, transaminase increase (placebo: n=0; BIMZELX: n=3 (2.3%) for each), and fatigue (placebo: n=1 (0.8%); BIMZELX: n=3 (2.3%)).

Specific Adverse Reactions

Suicidal Ideation and Behavior:The neuropsychiatric inclusion/exclusion criteria were the same in non-radiographic axial spondyloarthritis trials as in PSO.

During the first 16 weeks of the placebo controlled clinical trial (Trial nr-axSpA-1), no subjects in the BIMZELX or placebo group reported suicidal ideation on the C-SSRS. During the entire clinical trial program for nr-axSpA (398 patient-years), there were no cases of suicidal ideations. One suicide attempt (1/244; 0.25/100 patient-years) was reported in a BIMZELX-treated patient with pre-existing psychiatric conditions and recent life stressors.

Infections:During the placebo-controlled period of Trial nr-axSpA-1, infections were reported in 36% of subjects (144.8 per 100 patient-years) treated with BIMZELX compared with 25% of subjects (94.4 per 100 patient-years) receiving placebo. There were no reports of serious infections reported during the placebo-controlled period of the trial.

During the combined 52 week treatment period of Trial nr-axSpA-1, and subsequent open-label treatment, infections were reported in 68% of subjects treated with BIMZELX (78.0 per 100 patient-years). Serious infections were reported in 1.6% of subjects treated with BIMZELX (1.0 per 100 patient-years).

Inflammatory Bowel Disease:In the clinical trial in subjects with non-radiographic axial spondyloarthritis, subjects with active inflammatory bowel disease were excluded. In placebo-controlled, maintenance, and open label treatment periods of this trial, which included 244 subjects exposed to BIMZELX accounting for 397 patient-years, adjudicated cases of new onset of inflammatory bowel disease occurred in 1 subject (Ulcerative Colitis; 0.26 per 100 patient-years); this case of ulcerative colitis was nonserious and did not result in discontinuation of therapy.

Liver Biochemical Abnormalities:During the placebo-controlled period of Trials nr-axSpA-1, liver serum transaminase elevations (> 3 times the upper limit of normal [ULN]) occurred in 1.6% of subjects treated with BIMZELX versus 0.8% of subjects receiving placebo. Elevated liver serum transaminases resolved during continued treatment or after discontinuation of BIMZELX.

Safety through Week 52

During the maintenance period (Week 16 through Week 52 of Trial nr-axSpA-1), adverse reactions were consistent with those observed during the initial 16 weeks of treatment and with the overall safety profile of BIMZELX.

Ankylosing Spondylitis Clinical Trials

BIMZELX was evaluated in a placebo-controlled trial (Trial AS-1) in subjects with ankylosing spondylitis (221 subjects on BIMZELX and 111 subjects on placebo). The safety profile observed in subjects with ankylosing spondylitis treated with BIMZELX was overall similar to the safety profile seen in subjects with psoriatic arthritis, except for injection site pain, rash (placebo: n=1 (0.9%); BIMZELX: n=6 (2.7%), for each) and vulvovaginal mycotic infection (placebo: n=0; BIMZELX: n=5 (2.3%)).

Specific Adverse Reactions

Suicidal Ideation and Behavior:The neuropsychiatric inclusion/exclusion criteria were the same in AS trials as in PSO.

During the first 16 weeks of the placebo controlled clinical Trial AS-1, no subjects in the BIMZELX or placebo group reported suicidal ideation on the C-SSRS. During the entire clinical trial program for AS (1,844 patient-years), there was 1 case of suicidal ideation (1/684; 0.05/100 patient-years) reported in a subject with pre-existing psychiatric conditions.

Infections:During the placebo-controlled period of Trial AS-1, infections were reported in 28% of subjects (110.3 per 100 patient-years) treated with BIMZELX compared with 23% of subjects (83.7 per 100 patient-years) receiving placebo. Serious infections occurred in 1 (0.5%) subject (1.5 per 100 patient-years) treated with BIMZELX and 1 (0.9%) subject (2.9 per 100 patient-years) receiving placebo .

During the combined 52 week treatment period of Trial AS-1, and subsequent open-label treatment, infections were reported in 62% of subjects treated with BIMZELX (58.8 per 100 patient-years). Serious infections were reported in 2.7% of subjects treated with BIMZELX (1.5 per 100 patient-years).

Inflammatory Bowel Disease:In clinical trials in subjects with AS, subjects with active inflammatory bowel disease were excluded. In these phase 2/3 trials, which included 593 subjects exposed to BIMZELX accounting for 1,599 patient-years, adjudicated cases of new onset of inflammatory bowel disease (including ulcerative colitis (UC), Crohn's disease (CD) and IBD-undetermined) occurred in 6 subjects (0.38 per 100 patient-years); 4 cases were serious, and 3 cases resulted in discontinuation of therapy.

Liver Biochemical Abnormalities:During the placebo-controlled period of Trial AS-1, liver serum transaminase elevations (> 3 times the upper limit of normal [ULN]) occurred in 1.4% of subjects treated with BIMZELX versus 1.8% of subjects receiving placebo. Elevated liver serum transaminases resolved during continued treatment or after discontinuation of BIMZELX.

Safety through Week 52

During the maintenance period (Week 16 through Week 52 of Trial AS-1), adverse reactions were consistent with those observed during the initial 16 weeks of treatment and with the overall safety profile of BIMZELX.

Hidradenitis Suppurativa Clinical Trials

BIMZELX was evaluated in two placebo-controlled trials (Trial HS-1 and Trial HS-2) in 1,007 adult subjects with moderate to severe hidradenitis suppurativa (861 BIMZELX-treated subjects and 146 subjects receiving placebo) [see Clinical Studies (14.5)] . The safety profile observed in subjects with hidradenitis suppurativa treated with BIMZELX was overall similar to the safety profile seen in subjects with PSO treated with BIMZELX.

Upon completion of both trials, a total of 657 subjects enrolled in a long-term extension treatment period for up to an additional 188 weeks.

Specific Adverse Reactions

Suicidal Ideation and Behavior: The neuropsychiatric inclusion/exclusion criteria were the same in HS trials as in PSO.

Analysis of pooled C-SSRS data from the first 16 weeks of the placebo-controlled clinical trials indicated that 16/861 (1.9%) BIMZELX-treated subjects and 1/146 (0.7%) subjects receiving placebo reported suicidal ideation with an estimated relative risk of 2.70 (95% confidence interval: 0.36, 20.12). Subjects without a prior history of SI/B treated with BIMZELX also reported a higher rate of new-onset suicidal ideation on the C-SSRS than subjects treated with placebo (0.9% vs. 0%).

There were 2 reported cases of suicidal ideation that were adjudicated as suicide attempts (2/1,041; 0.15/100 patient-years). Both subjects had a history of neuropsychiatric disorders.

Infections:During the placebo-controlled period of Trials HS-1 and HS-2, infections were reported in 33% of subjects (132.2 per 100 patient-years) treated with BIMZELX compared with 21% of subjects (76.4 per 100 patient-years) receiving placebo. Serious infections occurred in 0.1% of subjects (0.4 per 100 patient-years) treated with BIMZELX and 0% of subjects receiving placebo .

The most commonly reported infections were comparable to those reported in subjects with PSO. Oral candidiasis occurred in 7.8% of subjects (26.7 per 100 patient years) treated with BIMZELX 320 mg Q2W, 3.9% of subjects (12.9 per 100 patient-years) treated with BIMZELX 320 mg Q4W, and 0 subjects receiving placebo. Other candida infections occurred in 3.6% of subjects (12.2 per 100 patient-years) treated with BIMZELX 320 mg Q2W, 6.7% of subjects (22.6 per 100 patient-years) treated with BIMZELX 320 mg Q4W, and 0 subjects receiving placebo. Tinea infections occurred in 3.1% of subjects (10.4 per 100 patient-years) treated with BIMZELX 320 mg Q2W, 2.5% of subjects (8.1 per 100 patient-years) treated with BIMZELX 320 mg Q4W, and 0.7% (2.3 per 100 patient-years) receiving placebo.

During the combined placebo-controlled, maintenance treatment periods and open-label extension treatment periods of Trials HS-1 and HS-2, infections were reported in 68% of subjects treated with BIMZELX (104.7 per 100 patient-years). Serious infections were reported in 2.1% of subjects treated with BIMZELX (1.7 per 100 patient-years).

Inflammatory Bowel Disease:In clinical trials in subjects with hidradenitis suppurativa, subjects with active inflammatory bowel disease were excluded. During the combined placebo-controlled, maintenance, and open-label extension treatment periods of Trials HS-1 and HS-2, which included 995 subjects exposed to BIMZELX accounting for 1,272 patient-years, adjudicated cases of new onset of inflammatory bowel disease (including ulcerative colitis (UC), Crohn's disease (CD) and undetermined) occurred in 5 subjects (0.39 per 100 patient-years); 3 of these cases were serious, all of which resulted in discontinuation of therapy. Additionally, flares of pre-existing IBD occurred in 2 subjects, which resulted in discontinuation of BIMZELX in both.

Liver Biochemical Abnormalities:During the placebo-controlled period of Trials HS-1 and HS-2, liver serum transaminase elevations (> 3 times the upper limit of normal [ULN]) occurred in 1.2% of subjects treated with BIMZELX versus 0% of subjects receiving placebo. Elevated liver serum transaminases resolved during continued treatment or after discontinuation of BIMZELX.

Safety through Week 48

During the maintenance period (Week 16 through Week 48 of Trials HS-1 and HS-2), adverse reactions were consistent with those observed during the initial 16 weeks of treatment and with the overall safety profile of BIMZELX.

6.2 Postmarketing Experience

The following adverse reactions have been reported during post-approval use of BIMZELX. Because they are reported voluntarily from a population of uncertain size, it is not always possible to reliably estimate their frequency or establish a causal relationship to drug exposure.

Infections:conjunctivitis, esophageal candidiasis

7 DRUG INTERACTIONS

CYP450 Substrates

The formation of CYP450 enzymes can be altered by increased levels of certain cytokines (e.g., IL-1, IL-6, IL-10, TNFα, IFN) during chronic inflammation. Treatment with BIMZELX may modulate serum levels of some cytokines.

Therefore, upon initiation or discontinuation of BIMZELX in patients who are receiving concomitant drugs which are CYP450 substrates, particularly those with a narrow therapeutic index, consider monitoring for effect (e.g., for warfarin) or drug concentration (e.g., for cyclosporine) and consider dosage modification of the CYP450 substrate.

Population pharmacokinetic (PK) data analyses indicated that the clearance of BIMZELX was not impacted by concomitant administration of cDMARDs including methotrexate, or by prior exposure to biologics.

8 USE IN SPECIFIC POPULATIONS

8.1 Pregnancy

Pregnancy Exposure Registry

There is a pregnancy exposure registry that monitors pregnancy outcomes in women exposed to BIMZELX during pregnancy. For more information, healthcare providers or patients can contact the Organization of Teratology Information Specialists (OTIS) AutoImmune Diseases Study at 1-877-311-8972 or visit http://mothertobaby.org/pregnancy-studies/.

Risk Summary

Available data from case reports on BIMZELX use in pregnant women are insufficient to evaluate for a drug associated risk of major birth defects, miscarriage, or other adverse maternal or fetal outcomes. Transport of human IgG antibody across the placenta increases as pregnancy progresses and peaks during the third trimester; therefore, BIMZELX may be transmitted from the mother to the developing fetus (see Clinical Considerations) . In an enhanced pre- and postnatal development study, no adverse developmental effects were observed in infants born to pregnant monkeys after subcutaneous administration of bimekizumab-bkzx during the period of organogenesis through parturition at doses up to 38 times the maximum recommended human dose (MRHD) (see Data) .

All pregnancies have a background risk of birth defect, loss, or other adverse outcomes. The background risk of major birth defects and miscarriage for the indicated population is unknown. In the U.S. general population, the estimated background risk of major birth defects and miscarriage in clinically recognized pregnancies is 2% to 4% and 15% to 20%, respectively.

Clinical Considerations

Fetal/Neonatal Adverse Reactions:Because bimekizumab-bkzx may interfere with immune response to infections, risks and benefits should be considered prior to administering live vaccines to infants exposed to BIMZELX in utero. There are no data regarding infant serum levels of bimekizumab-bkzx at birth and the duration of persistence of bimekizumab-bkzx in infant serum after birth. Although a specific timeframe to delay live virus immunizations in infants exposed in utero is unknown, a minimum of 4 months after birth may be considered because of the half-life of the product.

Data

Animal Data:An enhanced pre- and postnatal developmental toxicity study was conducted in cynomolgus monkeys. Pregnant cynomolgus monkeys were administered subcutaneous doses of bimekizumab-bkzx of 20 or 50 mg/kg/week from gestation day 20 to parturition and the cynomolgus monkeys (mother and infants) were monitored for 6 months after delivery. No maternal toxicity was noted in this study. There were no treatment-related effects on growth and development, malformations, developmental immunotoxicology or neurobehavioral development. The no observed adverse effect level (NOAEL) for both maternal and developmental toxicity was identified as 50 mg/kg/week (38 times the MRHD, based on mg/kg comparison of 1.33 mg/kg/week administered as a 320 mg dose to a 60 kg individual once every 4 weeks).

8.2 Lactation

Risk Summary

There are no data on the presence of bimekizumab-bkzx in human or animal milk, the effects on the breastfed infant, or the effects on milk production. Endogenous IgG and monoclonal antibodies are transferred in human milk. The effects of local gastrointestinal exposure and limited systemic exposure in the breastfed infant to bimekizumab-bkzx are unknown. The developmental and health benefits of breastfeeding should be considered along with the mother's clinical need for BIMZELX and any potential adverse effects on the breastfed infant from BIMZELX or from the underlying maternal condition.

8.4 Pediatric Use

The safety and effectiveness of BIMZELX in pediatric patients have not been established.

8.5 Geriatric Use

Of the 1,789 subjects with plaque psoriasis that were exposed to BIMZELX, a total of 153 subjects were 65 years of age or older, and 18 subjects were 75 years of age or older. Although no differences in safety or effectiveness were observed between subjects 65 years of age or older and younger adult subjects, clinical trials in PSO did not include sufficient numbers of subjects aged 65 years and over to determine whether they respond differently from younger adult subjects .

Of the 1,197 subjects with PsA that were exposed to BIMZELX, a total of 148 were 65 years of age and older. Although no differences in safety or effectiveness were observed between subjects 65 years of age or older and younger adult subjects, clinical trials in PsA did not include sufficient numbers of subjects aged 65 years and over to determine whether they respond differently from younger adult subjects .

Of the 244 subjects with nr-axSpA that were exposed to BIMZELX, a total of 6 were 65 years of age and older. Although no differences in safety or effectiveness were observed between subjects 65 years of age or older and younger adult subjects, the clinical trial in nr-axSpA did not include sufficient numbers of subjects aged 65 years and over to determine whether they respond differently from younger adult subjects .

Of the 330 subjects with AS that were exposed to BIMZELX, a total of 11 were 65 years of age and older. Although no differences in safety or effectiveness were observed between subjects 65 years of age or older and younger adult subjects, the clinical trial in AS did not include sufficient numbers of subjects aged 65 years and over to determine whether they respond differently from younger adult subjects .

Of the 995 subjects with hidradenitis suppurativa that were exposed to BIMZELX, a total of 18 were 65 years of age and older. Although no differences in safety or effectiveness were observed between subjects 65 years of age or older and younger adult subjects, clinical trials in HS did not include sufficient numbers of subjects aged 65 years and over to determine whether they respond differently from younger adult subjects .

11 DESCRIPTION

Bimekizumab-bkzx, an interleukin-17 A and F antagonist, is a recombinant humanized immunoglobulin G1 (IgG1) monoclonal antibody. Bimekizumab-bkzx is produced by recombinant DNA technology in Chinese Hamster Ovary cells, and has an approximate molecular weight of 150 kDa.

BIMZELX (bimekizumab-bkzx) injection is a sterile, preservative-free, clear to slightly opalescent, and colorless to pale brownish-yellow solution for subcutaneous use.

Each BIMZELX 1 mL (160 mg/mL) prefilled syringe or prefilled autoinjector delivers 1 mL containing 160 mg bimekizumab-bkzx, glacial acetic acid (1.23 mg), glycine (16.5 mg), polysorbate 80 (0.4 mg), sodium acetate (2.83 mg), and Water for Injection, USP at pH 5.1.

Each BIMZELX 2 mL (160 mg/mL) prefilled syringe or prefilled autoinjector delivers 2 mL containing 320 mg bimekizumab-bkzx, glacial acetic acid (2.46 mg), glycine (33.0 mg), polysorbate 80 (0.8 mg), sodium acetate (5.65 mg), and Water for Injection, USP at pH 5.1.

12 CLINICAL PHARMACOLOGY

12.1 Mechanism of Action

Bimekizumab-bkzx is a humanized immunoglobulin IgG1/ κ monoclonal antibody with two identical antigen binding regions that selectively bind to human interleukin 17A (IL-17A), interleukin 17F (IL-17F), and interleukin 17-AF cytokines, and inhibits their interaction with the IL-17 receptor complex. IL-17A and IL-17F are naturally occurring cytokines that are involved in normal inflammatory and immune responses. Bimekizumab-bkzx inhibits the release of proinflammatory cytokines and chemokines.

12.2 Pharmacodynamics

Elevated levels of IL-17A and IL-17F are found in lesional psoriatic skin, and lesional skin in HS. Bimekizumab-bkzx exposure-response relationships to serum biomarkers, including IL-17A and IL-17F, and the time course of such pharmacodynamic responses are unknown.

Immune Response to Inactivated or Non-Live Vaccines

Healthy individuals who received a single 320 mg dose of BIMZELX two weeks prior to vaccination with an inactivated seasonal influenza vaccine had similar antibody responses compared to individuals who did not receive BIMZELX prior to vaccination. The effectiveness of inactivated seasonal influenza vaccines and other inactivated and non-live vaccines has not been evaluated in patients treated with BIMZELX.

12.3 Pharmacokinetics

Bimekizumab-bkzx pharmacokinetics are comparable in adult patients with moderate to severe plaque psoriasis, psoriatic arthritis, non-radiographic axial spondyloarthritis, and ankylosing spondylitis.

The median peak plasma concentration of bimekizumab-bkzx was 25 (range: 12-50) μg/mL and was reached in 3-4 days. Bimekizumab-bkzx exhibited dose-proportional pharmacokinetics in patients with plaque psoriasis over a dose range of 64 mg to 480 mg (0.2 to 1.5 times the approved recommended dosage) following subcutaneous administration.

The median steady-state trough concentration of bimekizumab-bkzx was approximately 40% lower in HS subjects than that of PSO subjects.

Absorption

The absolute bioavailability of bimekizumab-bkzx was 70% in healthy subjects.

Distribution

The median volume of distribution at steady state was 11.2 L in subjects with moderate to severe plaque psoriasis. The volume of distribution in subjects with moderate to severe hidradenitis suppurativa was estimated to be approximately 18% higher than in subjects with moderate to severe plaque psoriasis.

Elimination

The median (coefficient of variation %) clearance (CL/F) of bimekizumab-bkzx was 0.337 L/day (32.7%). The mean terminal elimination half-life was 23 days, with clearance independent of dose. The apparent clearance in subjects with moderate to severe hidradenitis suppurativa was estimated to be approximately 31% higher than in subjects with moderate to severe plaque psoriasis.

Metabolism:Bimekizumab-bkzx is expected to be degraded into small peptides by catabolic pathways.

Specific Populations

No significant differences in the pharmacokinetics of bimekizumab-bkzx were observed based on age (≥18 years).

Body Weight:The average plasma concentration in adult subjects weighing ≥120 kg was predicted to be at least 30% lower than those weighing < 120 kg (median of 87 kg) [see Dosage and Administration (2.2)].

12.6 Immunogenicity

The observed incidence of anti-drug antibodies (ADA) is highly dependent on the sensitivity and specificity of the assay. Differences in assay methods preclude meaningful comparisons of the incidence of ADA in the studies described below with the incidence of ADA in other studies, including those of BIMZELX or of other bimekizumab products.

Across the pivotal trials in all indications, there was no identified clinically significant effect of anti-bimekizumab-bkzx antibodies, including neutralizing anti-drug antibodies, on safety or effectiveness of BIMZELX.

Plaque Psoriasis

During the 52–56-week treatment period in Trial Ps-1, Trial Ps-2, and Trial Ps-3 [see Clinical Studies (14.1)], 116/257 (45%) of BIMZELX-treated subjects (at the recommended dosage) developed anti-bimekizumab-bkzx antibodies (also referred to as ADA). Of the BIMZELX-treated subjects who developed ADA in these trials, approximately 16% had neutralizing antibodies.

Psoriatic Arthritis

During the 52-week treatment period in Trial PsA-1 [see Clinical Studies (14.2)] , 201/431 (47%) of subjects treated with BIMZELX had ADA, and 18% had neutralizing ADA.

Non-Radiographic Axial Spondyloarthritis

During the 52-week treatment period in Trial nr-axSpA-1 [see Clinical Studies (14.3)], 68/119 (57%) of BIMZELX-treated subjects had anti-bimekizumab-bkzx ADA, and approximately 25% had neutralizing ADA.

Ankylosing Spondylitis

During the 52-week treatment period in Trial AS-1 [see Clinical Studies (14.4)], 86/194 (44%) of BIMZELX-treated subjects had anti-bimekizumab-bkzx ADA, and approximately 20% had neutralizing ADA.

Hidradenitis Suppurativa

During the 48-week treatment period in Trials HS-1 and HS-2 [see Clinical Studies (14.5)], 171/291 (59%) of BIMZELX-treated subjects had anti-bimekizumab-bkzx ADA, and of those who developed ADA, approximately 63% had neutralizing ADA.

13 NONCLINICAL TOXICOLOGY

13.1 Carcinogenesis, Mutagenesis, Impairment of Fertility

Carcinogenicity and mutagenicity studies have not been conducted with bimekizumab-bkzx.

No effects on fertility parameters such as effects on reproductive organs, menstrual cycle length, or sperm analysis were observed in sexually mature cynomolgus monkeys that were subcutaneously administered 200 mg/kg/week bimekizumab-bkzx (150 times the MRHD, based on mg/kg comparison) for 26 weeks. The monkeys were not mated to evaluate fertility.

14 CLINICAL STUDIES

14.1 Plaque Psoriasis

Three multicenter, randomized, double-blind trials [Trial Ps-1 (NCT03370133), Trial Ps-2 (NCT03410992), and Trial Ps-3 (NCT03412747)] enrolled a total of 1,480 subjects 18 years of age and older with moderate to severe plaque psoriasis who had a body surface area (BSA) involvement of ≥10%, an Investigator's Global Assessment (IGA) score of ≥3 ("moderate") in the overall assessment of psoriasis on a severity scale of 0 to 4, and a Psoriasis Area and Severity Index (PASI) score ≥12.

In Trial Ps-1, 567 subjects were randomized to receive either BIMZELX 320 mg by subcutaneous injection every 4 weeks, ustekinumab (for subjects weighing ≤100kg, 45 mg initially and 4 weeks later, then every 12 weeks; for subjects weighing >100kg, 90 mg initially and 4 weeks later, then every 12 weeks), or placebo through Week 52. At Week 16, subjects originally randomized to placebo received BIMZELX 320 mg every 4 weeks through Week 52.

In Trial Ps-2, 435 subjects were randomized to either BIMZELX 320 mg by subcutaneous injection every 4 weeks or placebo. At Week 16, subjects who achieved a PASI 90 response continued into a 40-week randomized withdrawal period. Subjects originally randomized to BIMZELX 320 mg every 4 weeks were re-randomized to either BIMZELX 320 mg every 4 weeks or BIMZELX 320 mg every 8 weeks or placebo. Subjects originally randomized to placebo continued to receive placebo if they were PASI 90 responders. Subjects who did not achieve a PASI 90 response at week 16 entered an open-label escape arm and received BIMZELX 320 mg every 4 weeks for 12 weeks. Subjects who relapsed, defined as having a less than PASI 75 response compared to baseline, during the randomized withdrawal period also entered the 12-week escape arm.

In Trial Ps-3, 478 subjects were randomized to receive either BIMZELX 320 mg by subcutaneous injection every 4 weeks through week 56, BIMZELX 320 mg every 4 weeks through week 16 followed by BIMZELX every 8 weeks through week 56, or adalimumab (80 mg as an initial dose followed by 40 mg every other week starting 1 week after initial dose through Week 24) followed by BIMZELX 320 mg every 4 weeks through Week 56.

In Trial Ps-1, Trial Ps-2, and Trial Ps-3, 71% of the subjects were male and 84% of the subjects were White, with a mean age of 45 years and a mean weight of 89 kg. At baseline, subjects had a median baseline PASI score of 18, median baseline for BSA of 20%, and baseline IGA score of 4 ("severe") in 33% of subjects. A total of 93% subjects had psoriasis of the scalp (Scalp IGA score of ≥1) and a total of 26% of subjects had a history of psoriatic arthritis. Additionally, 38% had received prior biologic therapy.

Clinical Response at Week 16 (Trial Ps-1 and Trial Ps-2)

Trial Ps-1 and Trial Ps-2 responses at Week 16 compared to placebo for the two co-primary endpoints:

- The proportion of subjects who achieved an IGA score of 0 ("clear") or 1 ("almost clear") with at least a 2-grade improvement from baseline
- The proportion of subjects who achieved at least a 90% reduction from baseline PASI (PASI 90)

Secondary endpoints included the proportion of subjects who achieved PASI 100, IGA 0, and Scalp IGA response (defined as Scalp IGA score of 0 [clear] or 1 [almost clear] with at least 2-grade of improvement from baseline) at Week 16, and PASI 75 at Week 4. In addition, secondary endpoints included assessment of psoriasis symptoms (itching, pain, and scaling) measured by the Patient Symptom Diary (PSD) at Week 16.

The proportion of subjects who achieved IGA 0 or 1, PASI 90, IGA 0, and PASI 100 response at Week 16 are presented in Table 3.

Table 3: Efficacy Results at Week 16 in BIMZELX or Placebo-Treated Adults with Plaque Psoriasis in Trial Ps-1 and Trial Ps-2
 | Trial Ps-1 |  | Trial Ps-2
 | BIMZELX 320 mg every 4 weeks (N=321) n (%) | Placebo (N=83) n (%) | BIMZELX 320 mg every 4 weeks (N=349) n (%) | Placebo (N=86) n (%)
IGA 0 or 1 ("clear" or "almost clear") [Co-primary endpoints] | 270 (84%) | 4 (5%) | 323 (93%) | 1 (1%)
Difference (95% CI) | 79% (73%, 85%) |  | 91% (88%, 95%)
PASI 90 | 273 (85%) | 4 (5%) | 317 (91%) | 1 (1%)
Difference (95% CI) | 80% (74%, 86%) |  | 90% (86%, 93%)
IGA 0 ("clear") | 188 (59%) | 0 (0%) | 243 (70%) | 1 (1%)
Difference (95% CI) | 59% (53%, 64%) |  | 69% (64%, 74%)
PASI 100 | 188 (59%) | 0 (0%) | 238 (68%) | 1 (1%)
Difference (95% CI) | 59% (53%, 64%) |  | 67% (62%, 73%)

Examination of age, gender, race, baseline IGA score and previous treatment with systemic or biologic agents did not identify differences in response to BIMZELX among these subgroups at Week 16.

A greater proportion of subjects randomized to BIMZELX achieved PASI 75 at Week 4 in both trials compared to placebo. In Trial Ps-1, 77% of subjects treated with BIMZELX achieved PASI 75 compared to 2% treated with placebo. In Trial Ps-2, 76% of subjects treated with BIMZELX achieved PASI 75 compared to 1% treated with placebo.

Among subjects with Scalp IGA score of at least 2 at baseline, a greater proportion of subjects randomized to BIMZELX achieved Scalp IGA response at Week 16 in both trials compared to placebo. In Trial Ps-1, 84% (240/285) of subjects treated with BIMZELX achieved Scalp IGA response compared to 15% (11/72) of placebo treated subjects. In Trial Ps-2, 92% (286/310) of subjects treated with BIMZELX achieved Scalp IGA response compared to 7% (5/74) of placebo treated subjects.

Maintenance and Durability of Response

In Trial Ps-2, subjects randomized to BIMZELX every 4 weeks at Week 0 and who were PASI 90 responders at Week 16 were re-randomized to either continue treatment with BIMZELX every 4 weeks, switched to BIMZELX every 8 weeks, or be withdrawn from therapy (i.e., received placebo).

Figure 1 and Figure 2 present the percentage of subjects maintaining IGA score of 0 ("Clear") or 1 ("Almost Clear") and PASI 90, respectively, through Week 56 after re-randomization at Week 16.

Figure 1: Percentage of Subjects Maintaining IGA 0 or 1 through Week 56 after Re-Randomization at Week 16

For IGA 0 or 1 responders at Week 16 who were re-randomized to treatment withdrawal (i.e., placebo), the median time to loss of IGA 0 or 1 response was approximately 24 weeks. Among these subjects with IGA score of 2 at retreatment, 58% (14/24) achieved IGA score of 0 within 12 weeks of restarting treatment with BIMZELX 320 mg every 4 weeks. Among these subjects with IGA score ≥ 3 at retreatment, 87% (34/39) regained IGA 0 or 1 response with at least 2-grade improvement from retreatment within 12 weeks of restarting treatment with BIMZELX 320 mg every 4 weeks.

Figure 2: Percentage of Subjects Maintaining PASI 90 through Week 56 after Re-Randomization at Week 16

For PASI 90 responders at Week 16 who were re-randomized to treatment withdrawal (i.e., placebo), the median time to loss of PASI 90 response was approximately 24 weeks.

Patient Reported Outcomes

Greater improvements in itch, pain, and scaling at Week 16 with BIMZELX compared to placebo were observed in both trials as measured by the Patient Symptom Diary (PSD).

14.2 Psoriatic Arthritis

The safety and efficacy of BIMZELX were assessed in 1,112 subjects in two multicenter, randomized, double-blind, placebo-controlled studies [Trial PsA-1 (NCT 03895203) and Trial PsA-2 (NCT 03896581)] in subjects 18 years and older with active psoriatic arthritis (PsA).

Subjects in these studies had a diagnosis of PsA of at least 6 months based on Classification Criteria for Psoriatic Arthritis (CASPAR), a median duration of 4.6 years at baseline, and active disease with ≥3 tender joint count and ≥3 swollen joint count. Subjects with each subtype of PsA were enrolled in these studies, including polyarticular symmetric arthritis (63.5%), oligoarticular asymmetric arthritis (25.9%), distal interphalangeal joint predominant (4.4%), spondylitis predominant (4.2%), and arthritis mutilans (1.5%). At baseline, 56% of subjects had ≥3% Body Surface Area (BSA) with active plaque psoriasis. At baseline across both studies, 32% and 12% of subjects had enthesitis and dactylitis, respectively, 58% of subjects had psoriatic nail disease, and 53% of subjects were receiving concomitant methotrexate.

The PsA-1 study evaluated 852 biologic-naïve subjects, who were treated with either BIMZELX 160 mg every 4 weeks up to Week 52, adalimumab 40 mg every 2 weeks up to Week 52 (active reference arm), or placebo. Subjects receiving placebo were switched to BIMZELX every 4 weeks at Week 16 to Week 52. In this study, 78% of subjects had received prior treatment with ≥ 1 conventional DMARDs (cDMARDs), and 22 % of subjects had no prior treatment with cDMARDs. At baseline, 58% of subjects were receiving concomitant methotrexate (MTX), 11% were receiving concomitant cDMARDs other than MTX, and 31% were receiving no cDMARDs. The PsA-2 study evaluated 400 anti-TNFα experienced subjects (inadequate response or intolerance to treatment), who were treated with BIMZELX 160 mg every 4 weeks or placebo up to Week 16. In this study, 43% of subjects were receiving concomitant MTX, 8% were receiving concomitant cDMARDs other than MTX, and 50% were receiving no cDMARDs.

For both studies, the primary endpoint was the proportion of subjects who achieved an America College of Rheumatology (ACR) 50 response at Week 16.

Clinical Response

In both studies, treatment with BIMZELX resulted in significant improvement in disease activity, as measured by ACR, compared to placebo at Week 16 (see Table 4). Responses in Trial PsA-2 (anti-TNF experienced) were similar to Trial PsA-1.

Table 4: Clinical Responses at Week 16 in Trial PsA-1 and Trial PsA-2
 | Trial PsA-1 – bDMARD naïve |  |  | Trial PsA-2 – anti-TNFα experienced
Endpoint | BIMZELX 160 mg Q4W N=431 n (%) | Placebo N=281 n (%) | Difference from Placebo [95% CI based on normal approximation] (95% CI) | BIMZELX 160 mg Q4W N=267 n (%) | Placebo N=133 n (%) | Difference from Placebo (95% CI)
ACR 20 Response
Week 16 | 268 (62.2) | 67 (23.8) | 38.3 (31.6, 45.1) | 179 (67.0) | 21 (15.8) | 51.3 (42.9, 59.6)
ACR 50 Response
Week 16 | 189 (43.9) [Multiplicity-controlled p<0.001] | 28 (10.0) | 33.9 (28.0, 39.7) | 116 (43.4) | 9 (6.8) | 36.7 (29.4, 44.0)
ACR 70 Response
Week 16 | 105 (24.4) | 12 (4.3) | 20.1 (15.4, 24.8) | 71 (26.6) | 1 (0.8) | 25.8 (15.6, 35.7) [Exact 95% CI used]
CI= confidence interval

The percentage of subjects achieving ACR50 responses in Trial PsA-1 by visit through Week 16 is shown in Figure 3. Similar responses were seen in Trial PsA-2 up to Week 16.

Figure 3: Percent of Subjects Achieving ACR 50 Responses in Trial PsA-1 through Week 16

The results of the components of the ACR response criteria are shown in Table 5.

Table 5: Mean change from Baseline in ACR Component Scores at Week 16 in Trial PsA-1 and Trial PsA-2
 | Trial PsA-1 – bDMARD naïve |  | Trial PsA-2 – anti-TNFα experienced
 | Placebo (N=281) | BIMZELX 160 mg Q4W (N=431) | Placebo (N=133) | BIMZELX 160 mg Q4W (N=267)
Number of Swollen Joints
Baseline | 9.5 | 9.0 | 10.3 | 9.7
Mean change at Week 16 | -3.0 | -6.6 | -2.0 | -7.0
Number of Tender Joints
Baseline | 17.1 | 16.8 | 19.3 | 18.4
Mean change at Week 16 | -3.2 | -10.0 | -2.4 | -10.9
Patient's Assessment of Pain
Baseline | 56.8 | 53.7 | 61.7 | 58.3
Mean change at Week 16 | -6.2 | -23.6 | -4.5 | -27.7
Patient's Global Assessment
Baseline | 58.6 | 54.4 | 63.0 | 60.5
Mean change at Week 16 | -7.7 | -26.3 | -5.5 | -31.8
Physician Global Assessment
Baseline | 57.3 | 57.2 | 57.7 | 59.3
Mean change at Week 16 | -12.5 | -37.4 | -6.8 | -49.4
Health Assessment Questionnaire- Disability Index (HAQ-DI)
Baseline | 0.9 | 0.8 | 1.0 | 1.0
Mean Change at Week 16 | -0.1 | -0.3 [p<0.001 reference-based imputation versus placebo adjusted for multiplicity.] | -0.1 | -0.4
High Sensitivity C-reactive Protein (hsCRP) mg/L
Baseline | 11.4 | 8.7 | 11.6 | 12.4
Mean Change at Week 16 | -2.4 | -4.2 | 3.6 | -7.0
Multiple Imputation (MI) is used for all endpoints presented in Table 5.

Treatment with BIMZELX resulted in improvement in dactylitis and enthesitis in subjects with pre-existing dactylitis or enthesitis, compared to placebo.

In subjects with coexistent plaque psoriasis receiving BIMZELX, the skin lesions of psoriasis improved with treatment, relative to placebo, as measured by the Psoriasis Area Severity Index (PASI 90) at Week 16.

Radiographic Response

In Trial PsA-1, inhibition of progression of structural damage was assessed radiographically and expressed as the change from baseline in the Van der Heijde modified total Sharp Score (vdHmTSS) and its components, the Erosion Score (ES) and the Joint Space Narrowing score (JSN), at Week 16 (see Table 6).

BIMZELX significantly inhibited the rate of progression of joint damage at Week 16 in the overall population compared to placebo. The change from Baseline in erosion subscores contributed more to the change from Baseline in vdHmTSS total score than the change from Baseline in joint narrowing subscore. The percentage of subjects with no radiographic joint damage progression (defined as a change from baseline in mTSS of ≤0.0) from randomization to Week 16 was 77% for BIMZELX and 69% for placebo in the overall population. Similar responses were achieved in the population with elevated hsCRP and/or at least 1 bone erosion (75% for BIMZELX and 67% for placebo).

Table 6: Change in vdHmTSS in PsA-1 at Week 16
 | Placebo | BIMZELX 160 mg Q4W | Difference from Placebo (95% CI) [Unadjusted differences are shown]
Overall population | (N=269) | (N=420)
Baseline mean (SE) | 12.34 (1.37) | 12.47 (1.46)
Mean change from baseline at Week 16 (SE) | 0.32 (0.09) | 0.04 (0.04) [p≤0.001 versus placebo. p-values are based on reference-based imputation using difference in LS Mean using an ANCOVA model with treatment, bone erosion at Baseline and region as fixed effects and Baseline score as a covariate.] | -0.26 (-0.29, -0.23)

Physical Function

In both studies, subjects treated with BIMZELX showed statistically significant improvement from baseline in physical function compared with placebo as assessed by HAQ-DI at Week 16 (see Table 5). In both studies, a greater proportion of subjects achieved a reduction of at least 0.35 in HAQ-DI score from baseline in the BIMZELX group compared with placebo at Week 16.

Other Health Related Outcomes

Fatigue was assessed by Functional Assessment of Chronic Illness Therapy Fatigue Scale (FACIT-Fatigue). Additionally, in both studies at Week 16, subjects treated with BIMZELX showed improvements in FACIT-Fatigue scores.

14.3 Non-Radiographic Axial Spondyloarthritis

The efficacy and safety were assessed in 254 patients in one randomized, double-blind, placebo-controlled study [Trial nr-axSpA-1 (NCT03928704)] in adult subjects 18 years of age and older with active non-radiographic axial spondyloarthritis. Subjects had to have objective signs of inflammation with elevated C-reactive protein (CRP) level and/or evidence of sacroiliitis on Magnet Resonance Imaging (MRI). Subjects met ASAS classification criteria for axial spondyloarthritis and have active disease as defined by BASDAI greater than or equal to 4, spinal pain of greater than or equal to 4 (0-10 numeric rating scale (NRS)), and no definitive radiographic evidence of structural damage in the sacroiliac joints. At baseline, 73% of subjects had enthesitis. Subjects also had a history of inadequate response to 2 different non-steroidal anti-inflammatory drugs (NSAIDs), or intolerance or contraindication to NSAIDs. Approximately 24% of subjects were on concomitant cDMARDs. Overall, 11% of subjects had received previous treatment (failed or were intolerant to) with anti-TNF alpha agents.

Subjects were randomized to receive BIMZELX 160 mg or placebo every 4 weeks up to the completion of Week 16 assessments. Starting at Week 16, all subjects received BIMZELX every 4 weeks up to Week 52. The primary endpoint was at least 40% improvement in Assessment of Spondyloarthritis International Society (ASAS 40) at Week 16.

Clinical Response

In Trial nr-axSpA-1, treatment with BIMZELX resulted in significant improvements in the measure of disease activity compared to placebo at Week 16 (Table 7).

Table 7: Clinical Response in Trial nr-axSpA-1 at Week 16
 | BIMZELX 160 mg Q4W (N=128) | Placebo (N=126) | Difference from placebo (95% CI) [95% CI based on normal approximation]
 | n (%) | n (%)
ASAS 40 response | 61 (47.7%) [Multiplicity-controlled p<0.001] | 27 (21.4%) | 26.2 (15.0, 37.5)
ASAS 20 response | 88 (68.8%) | 48 (38.1%) | 30.7 (19.0, 42.3)
NRI is used
CI= confidence interval

Similar responses were seen regardless of prior anti-TNF alpha therapy. Treatment with BIMZELX resulted in improvement in enthesitis in subjects with pre-existing enthesitis.

The results of the main components of the ASAS 40 response criteria and other measures of disease activity are shown in Table 8.

Table 8: Components of the ASAS 40 Response Criteria and Other Measures of Disease Activity in nr-axSpA Subjects at Baseline and Week 16 in Trial nr-axSpA-1
 | BIMZELX 160 mg Q4W (N= 128) | Placebo (N=126)
ASAS Components
- Patient Global Assessment (0-10)
Baseline | 7.1 | 6.9
Mean Change from Baseline | -3.2 | -1.4
- Total Spinal Pain (0-10)
Baseline | 7.3 | 7.1
Mean Change from Baseline | -3.4 | -1.7
- BASFI (0-10)
Baseline | 5.5 | -2.5 [Multiplicity-controlled p<0.001]
Mean Change from Baseline | 5.3 | -1.0
- Inflammation (0-10) [Inflammation is the mean of patient-reported stiffness self-assessments (questions 5 and 6) in BASDAI]
Baseline | 7.0 | 6.9
Mean Change from Baseline | -3.6 | -1.9
Other Measures of Disease Activity
BASDAI Score
Baseline | 6.9 | 6.7
Mean Change from Baseline | -3.1 | -1.5
BASMI
Baseline | 2.9 | 3.0
Mean Change from Baseline | -0.4 | -0.1
hsCRP (mg/L)
Baseline | 11.1 | 10.2
Mean Change from Baseline | -6.7 | 0.0
BASFI = Bath Ankylosing Spondylitis Functional Index
BASMI = Bath Ankylosing Spondylitis Metrology Index
BASDAI = Bath Ankylosing Spondylitis Disease Activity Index
MI is used for all endpoints presented in Table 8

The percentage of subjects achieving ASAS 40 responses in Trial nr-axSpA-1 by visit through Week 16 is shown in Figure 4.

Figure 4: Percent of Subjects Achieving ASAS 40 Responses in Trial nr-axSpA-1 Week 16

Health Related Quality of Life

BIMZELX treated subjects showed significantly greater improvement compared to subjects receiving placebo at Week 16 in health-related quality of life as measured by the Ankylosing Spondylitis Quality of Life Questionnaire (ASQoL) score.

14.4 Ankylosing Spondylitis

The efficacy and safety were assessed in 332 patients in one randomized, double-blind, placebo-controlled study [Trial AS-1 (NCT03928743)] in adult subjects 18 years of age and older with active ankylosing spondylitis. Subjects had to have documented radiologic evidence (x-ray) fulfilling the Modified New York criteria for AS. Subjects had active disease as defined by BASDAI ≥4 and spinal pain ≥4 on a 0 to 10 numeric rating scale (NRS) (from BASDAI Item 2). Subjects also had a history of inadequate response to 2 different non-steroidal anti-inflammatory drugs (NSAIDs), or intolerance or contraindication to NSAIDs. Approximately 20% of subjects were on concomitant cDMARDs. Overall, 16% of subjects had received previous treatment (failed or were intolerant to) with anti-TNF alpha agents.

Subjects were randomized 2:1 to receive BIMZELX 160 mg or placebo every 4 weeks up to the completion of Week 16 assessments. Starting at Week 16, all subjects received BIMZELX every 4 weeks up to Week 52. The primary endpoint was at least 40% improvement in Assessment of Spondyloarthritis International Society (ASAS 40) at Week 16.

Clinical Response

In Trial AS-1, treatment with BIMZELX resulted in significant improvements in the measure of disease activity compared to placebo at Week 16 (Table 9).

Table 9: Clinical Response in Trial AS-1 at Week 16
 | BIMZELX 160 mg Q4W (N=221) | Placebo (N=111) | Difference from placebo (95% CI) [95% CI based on normal approximation]
 | n (%) | n (%)
ASAS 40 response | 99 (44.8%) [Multiplicity-controlled p<0.001] | 25 (22.5%) | 22.3 (12.1, 32.4)
ASAS 20 response | 146 (66.1%) | 48 (43.2%) | 22.8 (11.7, 34.0)
NRI is used
CI= confidence interval

Similar responses were seen regardless of prior anti-TNF alpha therapy. Treatment with BIMZELX resulted in improvement in enthesitis in subjects with pre-existing enthesitis.

The results of the main components of the ASAS 40 response criteria and other measures of disease activity are shown in Table 10.

Table 10: Components of the ASAS 40 Response Criteria and Other Measures of Disease Activity in Ankylosing Spondylitis Subjects at Baseline and Week 16 in Trial AS-1
 | BIMZELX 160 mg Q4W (N= 221) | Placebo (N=111)
ASAS Components
- Patient Global Assessment (0-10)
Baseline | 6.6 | 6.7
Mean Change from Baseline | -2.7 | -1.6
- Total Spinal Pain (0-10)
Baseline | 7.1 | 7.2
Mean Change from Baseline | -3.3 | -1.9
- BASFI (0-10)
Baseline | 5.3 | 5.2
Mean Change from Baseline | -2.2 [Multiplicity-controlled p<0.001] | -1.1
- Inflammation (0-10) [Inflammation is the mean of patient-reported stiffness self-assessments (questions 5 and 6) in BASDAI.;]
Baseline | 6.7 | 6.8
Mean Change from Baseline | -3.2 | -2.1
Other Measures of Disease Activity
BASDAI Score
Baseline | 6.4 | 6.5
Mean Change from Baseline | -2.9 | -1.9
BASMI
Baseline | 3.9 | 3.8
Mean Change from Baseline | -0.5 [Multiplicity-controlled p<0.006] | -0.2
hsCRP (mg/L)
Baseline | 14.7 | 13.6
Mean Change from Baseline | -8.6 | -2.2
BASFI = Bath Ankylosing Spondylitis Functional Index
BASMI = Bath Ankylosing Spondylitis Metrology Index
BASDAI = Bath Ankylosing Spondylitis Disease Activity Index
MI is used for all endpoints presented in Table 10

The percentage of subjects achieving ASAS 40 responses in Trial AS-1 by visit through Week 16 is shown in Figure 5.

Figure 5: Percent of Subjects Achieving ASAS 40 Responses in Trial AS-1 Through Week 16

Health Related Quality of Life

BIMZELX treated subjects showed significantly greater improvement compared to subjects receiving placebo at Week 16 in health-related quality of life as measured by the Ankylosing Spondylitis Quality of Life Questionnaire (ASQoL) score.

14.5 Hidradenitis Suppurativa

The safety and efficacy of BIMZELX were assessed in two Phase 3 multicenter, randomized, double-blind, placebo-controlled trials [Trial HS-1 (NCT04242446) and Trial HS-2 (NCT04242498)] in 1,014 adult subjects with moderate to severe HS of at least 6 months with Hurley Stage II or Hurley Stage III disease, and with ≥5 inflammatory lesions [i.e., number of abscesses plus number of inflammatory nodules (AN count)], and a history of inadequate response to a course of systemic antibiotics for the treatment of HS.

Subjects received BIMZELX 320 mg every 2 weeks (Q2W) for 48 weeks, or BIMZELX 320 mg every 4 weeks (Q4W) up to Week 48, or BIMZELX 320 mg Q2W to Week 16, followed by 320 mg Q4W up to Week 48, or placebo. At Week 16, subjects receiving placebo were switched to BIMZELX 320 mg Q2W to Week 48. Concomitant oral doxycycline, minocycline, or an equivalent systemic tetracycline for HS was allowed if the subject was on a stable dose regimen for 28 days prior to baseline.

In these trials, at baseline the mean age of all subjects was 37 years, 57% of subjects were female, 80% were White, 11% were Black or African American, and 4% were Asian; for ethnicity, 7% identified as Hispanic or Latino. Of the subjects enrolled in trials conducted in the United States, 33% were Black or African American. The mean BMI was 33, and 46% were current smokers. Subjects had a median disease duration of 5 years. Overall, 9% of subjects were receiving concomitant antibiotic therapy for HS, and 19% of subjects had received previous treatment with biologics. The proportion of Hurley Stage II and Stage III subjects were 56% and 44%, respectively. Additionally, the mean number of draining tunnels was 3.6 and mean AN count was 16.3.

The primary efficacy endpoint in both trials was the Hidradenitis Suppurativa Clinical Response 50 (HiSCR50) at Week 16, defined by at least a 50% reduction in total abscess and inflammatory nodule count with no increase in abscess or draining tunnel count relative to baseline. Secondary endpoints included the proportion of subjects who achieved HiSCR75 and HS-specific skin pain response as assessed by a 0 to 10 numeric rating scale (NRS).

Clinical Response at Week 16 (Trials HS-1 and HS-2)

In both trials, a higher proportion of BIMZELX-treated subjects achieved HiSCR50 and HiSCR75 compared to placebo (see Table 11).

Table 11: Efficacy Results in Adults with HS in Trials HS-1 and HS-2 at Week 16 [Subjects who initiated systemic antibiotics (new antibiotic or change in the dose/type of current antibiotic) for any reason or who discontinued due to adverse event or lack of efficacy are treated as non-responders at all subsequent visits. Other missing data were imputed via multiple imputation.]
 | Trial HS-1 |  | Trial HS-2
 | BIMZELX 320mg Q2W (N=289) | Placebo (N=72) | BIMZELX 320 mg Q2W (N=291) | Placebo (N=74)
HiSCR50 | 48% | 29% | 52% | 32%
Difference (95% CI) | 18% (6%, 30%) |  | 20% (8%, 32%)
HiSCR75 | 33% | 18% | 36% | 16%
Difference (95% CI) | 15% (4%, 27%) |  | 20% (10%, 31%)

Examination of age, gender, race, disease duration, weight, prior biologic therapy, systemic antibiotic use at baseline, Hurley stage, and smoking status did not identify meaningful differences in response to BIMZELX among these subgroups at Week 16.

Figure 6 presents the proportion of subjects achieving HiSCR50 response in Trials HS-1 and HS-2 by visit through Week 16.

Figure 6: HiSCR50 Response through Week 16 in Adults with HS in Trials HS-1 and HS-2

Subjects who initiated systemic antibiotics (new antibiotic or change in the dose/type of current antibiotic) for any reason through Week 16 or who discontinued due to adverse event or lack of efficacy are treated as non-responders at all subsequent visits. Other missing data were imputed via multiple imputation.

BIMZELX was associated with an improvement in patient-reported worst skin pain (lesion pain) based on the achievement of a reduction of at least 3 points (as measured on a 0 to 10 NRS) compared to placebo at Week 16.

16 HOW SUPPLIED/STORAGE AND HANDLING

How Supplied

BIMZELX (bimekizumab-bkzx) injection is a sterile, preservative-free, clear to slightly opalescent, and colorless to pale brownish-yellow solution. Each prefilled autoinjector or prefilled syringe contains 1 mL or 2 mL of a 160 mg/mL solution. The autoinjectors and prefilled syringes are not made with natural rubber latex. BIMZELX is supplied as:

BIMZELX autoinjector:

- NDC 50474-781-85: Carton of two 160 mg/mL single-dose autoinjectors. Each prefilled autoinjector is fixed with a 27 gauge ½ inch needle.
- NDC 50474-781-84: Carton of one 160 mg/mL single-dose autoinjector. The prefilled autoinjector is fixed with a 27 gauge ½ inch needle.
- NDC 50474-782-84: Carton of one 320 mg/2 mL (160 mg/mL) single-dose autoinjector fixed with a 27 gauge ½ inch needle.

BIMZELX prefilled syringe:

- NDC 50474-780-79: Carton of two 160 mg/mL single-dose prefilled syringes. Each prefilled syringe is fixed with a 27 gauge ½ inch needle with needle guard.
- NDC 50474-780-78: Carton of one 160 mg/mL single dose prefilled syringe. The prefilled syringe is fixed with a 27 gauge ½ inch needle with a needle guard.
- NDC 50474-783-78: Carton of one 320 mg/2 mL (160 mg/mL) single-dose prefilled syringe with a 27 gauge ½ inch needle.

Storage and Handling

Store cartons with BIMZELX refrigerated between 2°C to 8°C (36°F to 46°F). Keep the product in the original carton to protect it from light until the time of use. Do not freeze. Do not shake. Do not use beyond expiration date. BIMZELX does not contain a preservative; discard any unused portion.

When necessary, BIMZELX prefilled syringes or autoinjectors may be stored at room temperature up to 25°C (77°F) in the original carton for a single period of up to 30 days. Once BIMZELX prefilled syringes or autoinjectors have been stored at room temperature, do not place back in refrigerator. Write the date removed from the refrigerator in the space provided on the carton and discard if not used within a 30-day period.

17 PATIENT COUNSELING INFORMATION

Advise the patient and/or caregiver to read the FDA-approved patient labeling (Medication Guide and Instructions for Use).

Administration Instructions

Instruct patients or caregivers to perform the first self-injection under the supervision and guidance of a qualified healthcare professional for proper training in subcutaneous injection technique [see Dosage and Administration (2.9), Instructions for Use].

If two separate 160 mg injections are used to achieve the recommended dose, instruct patients or caregivers to administer each injection subcutaneously at a different anatomic location [see Dosage and Administration (2.9)] .

Instruct patients or caregivers in the technique of needle and syringe disposal [see Instructions for Use].

Advise patients if they forget to take their dose of BIMZELX to inject their dose as soon as they remember. Instruct patients to then take their next dose at the appropriate scheduled time [see Dosage and Administration (2.7)] .

Suicidal Ideation and Behavior

Instruct patients and their caregivers to monitor for the emergence of suicidal ideation and behavior and promptly seek medical attention if the patient experiences suicidal ideation or behavior; or new onset or worsening depression, anxiety, or other mood changes. Instruct patients to call the National Suicide and Crisis Lifeline at 988 if they experience suicidal ideation or behavior [see Warnings and Precautions (5.1)].

Infections

Inform patients that BIMZELX may lower the ability of their immune system to fight infections. Instruct patients of the importance of communicating any history of infections to the healthcare provider and contacting their healthcare provider if they develop any symptoms of an infection [see Warnings and Precautions (5.2)] .

Liver Biochemical Abnormalities

Inform patients that BIMZELX may increase the risk of elevated liver enzymes. Acute liver disease or cirrhosis may increase this risk. Advise patients that laboratory evaluation is needed prior to and periodically during treatment. Advise patients to hold the next dose of BIMZELX and call their healthcare provider right away, if signs or symptoms of liver dysfunction occur [see Warnings and Precautions (5.4)] .

Inflammatory Bowel Disease

Instruct patients to seek medical advice if they develop signs and symptoms of Crohn's disease or ulcerative colitis [see Warnings and Precautions (5.5)] .

Immunizations

Advise patients to avoid vaccination with live vaccines during BIMZELX treatment. Instruct patients to inform their healthcare practitioner that they are taking BIMZELX prior to a potential vaccination [see Warnings and Precautions (5.6)] .

Pregnancy

Advise patients that there is a pregnancy registry that monitors pregnancy outcomes in patients exposed to BIMZELX during pregnancy [see Use in Specific Populations (8.1)] .

Manufactured by:
UCB, Inc.
1950 Lake Park Drive Smyrna, GA 30080
US License No. 1736

MEDICATION GUIDE
BIMZELX®(bim zel'ex)
(bimekizumab-bkzx)
injection, for subcutaneous use

What is the most important information I should know about BIMZELX?
BIMZELX is a medicine that affects your immune system. BIMZELX may increase your risk of having serious side effects, including:

- Suicidal thoughts and behavior. New or worsening suicidal thoughts and behavior have happened in some people treated with BIMZELX.Get medical help right away or call the National Suicide and Crisis Lifeline at 988 if you, your caregiver or your family member notice in you any of the following symptoms:
  - new or worsening depression or anxiety
  - thoughts of suicide, dying, or hurting yourself
  - changes in behavior or mood
  - acting on dangerous impulses
  - attempt to commit suicide
- Infections. BIMZELX is a medicine that may lower the ability of your immune system to fight infections and may increase your risk of infections, including serious infections.
  - Your healthcare provider should check you for infections and tuberculosis (TB) before starting treatment with BIMZELX.
  - If your healthcare provider feels you are at risk for TB, you may be treated with medicine for TB before you begin treatment with BIMZELX and during your treatment with BIMZELX.
  - Your healthcare provider should watch you closely for signs and symptoms of TB during and after treatment with BIMZELX. Do not take BIMZELX if you have an active TB infection.

Before starting BIMZELX, tell your healthcare provider if you:

- are being treated for an infection
- have an infection that does not go away or keeps coming back
- have TB or have been in close contact with someone with TB
- think you have an infection or have symptoms of an infection such as:

- fever, sweats, or chills
- muscle aches
- cough
- shortness of breath
- blood in your phlegm

- weight loss
- warm, red, or painful skin or sores on your body different from your psoriasis
- diarrhea or stomach pain
- burning when you urinate or urinating more often than normal

After starting BIMZELX, call your healthcare provider right away if you have any of the signs of infection listed above.Do not use BIMZELX if you have any signs of infection unless you are instructed to by your healthcare provider.
See " What are the possible side effects of BIMZELX?" for more information about side effects.

What is BIMZELX?
BIMZELX is a prescription medicine used to treat:

- adults with moderate to severe plaque psoriasis who may benefit from taking injections or pills (systemic therapy) or treatment using ultraviolet light alone or with pills (phototherapy).
- adults with active psoriatic arthritis.
- adults with active non-radiographic axial spondyloarthritis with objective signs of inflammation.
- adults with active ankylosing spondylitis.
- adults with moderate to severe hidradenitis suppurativa.

It is not known if BIMZELX is safe and effective in children.

Before using BIMZELX, tell your healthcare provider about all of your medical conditions, including if you:

- have any of the conditions or symptoms listed in the section "What is the most important information I should know about BIMZELX?"
- have a history of depression, or suicidal thoughts or behavior
- have liver problems
- have inflammatory bowel disease (Crohn's disease or ulcerative colitis)
- have recently received or are scheduled to receive an immunization (vaccine). You should avoid receiving live vaccines during treatment with BIMZELX. Tell all your healthcare providers that you are being treated with BIMZELX before receiving a vaccine.
- are pregnant or plan to become pregnant. It is not known if BIMZELX can harm your unborn baby.
  - If you become pregnant while taking BIMZELX, you are encouraged to enroll in the Pregnancy Registry. The purpose of the pregnancy registry is to collect information about the health of you and your baby. Talk to your healthcare provider or call 1-877-311-8972 to enroll in this registry or visit http://mothertobaby.org/pregnancy-studies/.
- are breastfeeding or plan to breastfeed. It is not known if BIMZELX passes into your breast milk. Talk to your healthcare provider about the best way to feed your baby during treatment with BIMZELX.

Tell your healthcare provider about all the medicines you take, including prescription and over the counter medicines, vitamins and herbal supplements.

How should I use BIMZELX?
See the detailed " Instructions for Use" that comes with your BIMZELX for information on how to prepare and inject a dose of BIMZELX, and how to properly throw away (dispose of) used BIMZELX autoinjectors and prefilled syringes.

- Use BIMZELX exactly as prescribed by your healthcare provider.
- If you miss your BIMZELX dose, inject a dose as soon as you remember. Then, take your next dose at your regular scheduled time. Call your healthcare provider if you are not sure what to do.

What are the possible side effects of BIMZELX?
BIMZELX may cause serious side effects, including:

- See " What is important information I should know about BIMZELX?"
- Elevated liver enzyme levels.Your healthcare provider will do blood tests to check your liver enzyme levels before starting treatment and during treatment with BIMZELX. Your healthcare provider may temporarily stop or permanently stop your treatment with BIMZELX if you develop liver problems. Call your healthcare provider right away if you develop any signs or symptoms of liver problems, including:

- pain on the right side of your stomach-area
- feeling very tired
- loss of appetite
- nausea and vomiting

- itching
- dark urine
- light-colored stool
- yellowing of your skin or the whites of your eyes

- Inflammatory bowel disease.New cases of inflammatory bowel disease or "flare-ups" have happened with BIMZELX. If you have inflammatory bowel disease (Crohn's disease or ulcerative colitis), tell your healthcare provider if you have worsening disease symptoms during treatment with BIMZELX or develop new symptoms of stomach pain or diarrhea. Your healthcare provider will stop treatment with BIMZELX if you develop new or worsening signs of Crohn's disease or ulcerative colitis.

The most common side effects of BIMZELX in people treated for Psoriasis and Hidradenitis Suppurativa include:

- upper respiratory tract infections
- headache
- herpes simplex infections (cold sores in or around the mouth)
- small red bumps on your skin
- feeling tired

- fungal infections (oral thrush or infections in the mouth, throat, skin, nails, feet or genitals)
- pain, redness or swelling at injection site
- stomach flu (gastroenteritis)
- acne

The most common side effects of BIMZELX in people treated for psoriatic arthritis include:

- upper respiratory tract infections
- headache
- urinary tract infection

- oral thrush or infections in the mouth
- diarrhea

The most common side effects of BIMZELX in people treated for non-radiographic axial spondyloarthritis include:

- upper respiratory tract infections
- headache
- cough
- joint pain
- tonsilitis
- urinary tract infection

- oral thrush or infections in the mouth
- diarrhea
- feeling tired
- muscle aches
- liver enzyme increase

The most common side effects of BIMZELX in people treated for ankylosing spondylitis include:

- upper respiratory tract infections
- headache
- pain at injection site
- vaginal yeast infections

- oral thrush or infections in the mouth
- diarrhea
- rash

These are not all of the possible side effects of BIMZELX.
Call your doctor for medical advice about side effects. You may report side effects to FDA at 1-800-FDA-1088.

How should I store BIMZELX?

- Store BIMZELX in the refrigerator between 36°F to 46°F (2°C to 8°C).
- BIMZELX may be stored at room temperature up to 77°F (25°C) for up to 30 days in the original carton. Do notplace BIMZELX prefilled syringes or autoinjectors back in the refrigerator after they have been stored at room temperature.
- Write the date removed from the refrigerator in the space provided on the carton and throw away BIMZELX if it has been kept at room temperature and not been used within 30 days.
- Keep BIMZELX in the original carton until ready for use to protect from light.
- Do not freeze BIMZELX.
- Do not shake BIMZELX.
- Do not use BIMZELX past the expiration date printed on the carton.

Keep BIMZELX and all medicines out of the reach of children.

General information about the safe and effective use of BIMZELX.
Medicines are sometimes prescribed for purposes other than those listed in a Medication Guide. Do not use BIMZELX for a condition for which it was not prescribed. Do not give BIMZELX to other people, even if they have the same symptoms that you have. It may harm them. You can ask your pharmacist or healthcare provider for information about BIMZELX that is written for health professionals.

What are the ingredients in BIMZELX?
Active ingredient: bimekizumab-bkzx
Inactive ingredients: glacial acetic acid, glycine, polysorbate 80, sodium acetate and Water for Injection, USP.
Manufactured by:
UCB, Inc.
1950 Lake Park Drive Smyrna, GA 30080
US License No. 1736
For more information, go to www.BIMZELX.com or call 1-844-599-2273

This Medication Guide has been approved by the U.S. Food and Drug Administration.

Revised: November 2024

INSTRUCTIONS for USE BIMZELX®(bim zel' ex) (bimekizumab-bkzx) injection, for subcutaneous use single-dose autoinjector

This Instructions for Use contains information on how to inject BIMZELX.

Read this Instructions for Use before using the BIMZELX autoinjector and each time you get a refill. There may be new information. This information does not take the place of talking to your healthcare provider about your medical condition or treatment.

These instructions are for 1 injection only. You may need more than 1 injection at a time depending on your prescribed dose of BIMZELX. Each BIMZELX autoinjector is for one-time (single-dose) use only.

Important Information you Need to Know Before Injecting BIMZELX:

- Your healthcare provider should show you or a caregiver how to prepare and inject BIMZELX using the autoinjector for the first time. Do not inject yourself or someone else until you have been shown how to inject BIMZELX the right way. Call your healthcare provider if you have any questions.
- These instructions are for 1 injection only.
- The BIMZELX autoinjector has a needle safety feature that will be activated to cover the needle after the injection is finished. The needle safety feature will help to prevent needle stick injuries to anyone who handles the autoinjector after injection.
- Do notshare or reuse your BIMZELX autoinjector. You may give or get an infection.
- Do notremove the needle cap until just before you give the injection.
- If you have vision or hearing problems, do notuse the BIMZELX autoinjector without help from a caregiver.

How should I store BIMZELX autoinjector?

- Store the BIMZELX autoinjector in the refrigerator between 36°F to 46°F (2°C to 8°C).
- BIMZELX autoinjectors may be stored at room temperature up to 77°F (25°C) in the original carton for up to 30 days. Do notplace BIMZELX autoinjectors back in the refrigerator after they have been stored at room temperature.
- Write the date removed from the refrigerator in the space provided on the carton and throw away if it has been kept at room temperature and not used within 30 days.
- Keep BIMZELX in the original carton until ready for use to protect from light.
- Do not freeze BIMZELX.
- Do not shake BIMZELX.
- Do not use the BIMZELX autoinjector past the expiration date printed on the carton.

Keep BIMZELX autoinjectors and all medicines out of the reach of children.

BIMZELX autoinjector parts (see Figure A):

Supplies Needed for each BIMZELX injection

- 1 BIMZELX autoinjector. You may need 2 BIMZELX autoinjectors to give the prescribed dose.

Not provided in the BIMZELX autoinjector carton:

- 1 alcohol swab
- 1 clean cotton ball
- 1 sharps disposal container. See, " Step 12: Dispose of (throw away) the used BIMZELX autoinjector" at the end of this Instructions for Use.

Setting up for your BIMZELX injection.

Step 1: Take the BIMZELX autoinjector carton out of the refrigerator. Do notuse the BIMZELX autoinjector(s) if the carton seal is broken. Throw it away and get a new one.

- Keep the BIMZELX autoinjector in its original carton for 30 to 45 minutesto warm to room temperature. This will help to reduce discomfort when injecting.
  - Do notmicrowave the autoinjector, run hot water over it, or leave it in direct sunlight.
  - Do notshake the autoinjector.
  - Do nottake the cap off the autoinjector until you are ready to inject.

Step 2: Find a clean, flat, and well-lit work surface, like a table.

Step 3:Gather the supplies needed for your injection.

Step 4:Wash your hands well with soap and water and dry with a clean towel.

Step 5:Inspect the BIMZELX autoinjector (see Figure B):

- Remove the BIMZELX autoinjector from the carton.
- Make sure the name BIMZELX appears on the label.
  - Check the expiration date printed on the label.
  - Check the medicine through the Viewing Window. The medicine inside should be clear to slightly pearly, and colorless to pale brownish-yellow. You may see air bubble(s) in the liquid. This is normal.
- Do not use the BIMZELX autoinjector,throw it away and get a new one if:
  - The expiration date printed on the label has passed.
  - The medicine is cloudy, discolored, or has particles.
  - It looks damaged or has been dropped.

Choose and prepare your injection site.

Step 6: Choose and clean your injection site.

- The sites you may choose for your injection are:
  - your stomach area (abdomen) or your thigh (see Figure C).
  - the back of your arm (see Figure D). BIMZELX may be injected into the back of your arm by a healthcare provider or caregiver only.

- Do notinject into areas where the skin is tender, bruised, red, hard, thick, scaly, or affected by psoriasis , or within 2 inches of the belly button (navel).
- Choose a new injection site on the body each time you use BIMZELX. Do notuse the same injection site 2 times in a row.

Step 7: Prepare your skin

- Clean the injection site with an alcohol swab. Let the area dry completely. Do nottouch the cleaned area again before injecting.

Injecting BIMZELX.

Step 8: Remove the BIMZELX autoinjector cap.

- Hold the BIMZELX autoinjector firmly with one hand around the handle. Pull the cap straight off (away from) the autoinjector with the other hand (see Figure E). Although you cannot see the needle tip, it is now uncovered.
  - Putthe cap into an FDA-cleared sharps disposal container right away. You will not need it again.
  - Do nottouch the needle guard or put the cap back on as it could activate the autoinjector and you can stick yourself.

Step 9:Hold the BIMZELX autoinjector at a 90-degree angle to the cleaned injection site (see Figure F).

Step 10:Place the BIMZELX autoinjector flat against your skin, then firmly press the BIMZELX autoinjector down against your skin. You will hear a "click" sound. Your injection begins when the 1st"click" is heard (see Figure G) .

- Do notlift the autoinjector away from the skin.

Keep holding the BIMZELX autoinjector in place and pressed firmly against your skin. It will take about 15 seconds to receive your full dose.

- You will hear a 2nd"click" in about 15 seconds after you hear the first click.
- The second click tells you that all the medicine has been injected and your BIMZELX injection is finished. You should see the yellow color indicator filling the viewing window (see Figure H) .
- Important:When you remove the autoinjector, if the viewing window has not turned yellow this means you may not have received a full dose. Call your healthcare provider right away.

Step 11:Remove the BIMZELX autoinjector by carefully pulling the BIMZELX autoinjector straight up from your skin. The needle guard will automatically cover the needle. Do nottry to touch the needle.

- Press a clean cotton ball over the injection site for a few seconds. Do notrub the injection site. You may see slight bleeding or a drop of liquid. This is normal. You may cover the injection site with a small adhesive bandage, if needed.

Step 12: Dispose of (throw away) the used BIMZELX autoinjector (see Figure I).

- Put the used BIMZELX autoinjector in an FDA-cleared sharps disposal container right away after use. Do notthrow away (dispose of) the BIMZELX autoinjector in your household trash. If you do not have an FDA-cleared sharps disposal container, you may use a household container that is:
  - made of a heavy-duty plastic,
  - can be closed with a tight-fitting, puncture-resistant lid, without sharps being able to come out,
  - upright and stable during use,
  - leak-resistant, and
  - properly labeled to warn of hazardous waste inside the container.
- When your sharps disposal container is almost full, you will need to follow your community guidelines for the right way to dispose of your sharps disposal container. There may be state or local laws about how you should throw away needles and syringes. For more information about safe sharps disposal, and for specific information about sharps disposal in the state you live in, go to the FDA's website at: http://www.fda.gov/safesharpsdisposal.
- Do notrecycle your used sharps disposal container.

Step 13: Repeat steps 1 through 12 with a new BIMZELX autoinjector if you need to use 2 autoinjectors to give the prescribed dose.

- Make sure you select a new injection site on the body each time you use BIMZELX. Do notuse the same site that you used for your first injection.

You can sign up to receive sharps containers for BIMZELX autoinjector disposal at no additional cost by going to www.BIMZELX.comor call 1-844-599-2273.

Manufactured by:
UCB, Inc. 1950 Lake Park Drive Smyrna, GA 30080
US License No. 1736

This Instructions for Use has been approved by the U.S. Food and Drug Administration.

Issued: 9/2024

INSTRUCTIONS for USE BIMZELX®(bim zel' ex) (bimekizumab-bkzx) injection, for subcutaneous use single-dose prefilled syringe

This Instructions for Use contains information on how to inject BIMZELX.

Read this Instructions for Use before using the BIMZELX prefilled syringe and each time you get a refill. There may be new information. This information does not take the place of talking to your healthcare provider about your medical condition or treatment.

These instructions are for 1 injection only. You may need more than 1 injection at a time depending on your prescribed dose of BIMZELX.

Important Information you Need to Know Before Injecting BIMZELX:

- Your healthcare provider should show you or a caregiver how to prepare and inject BIMZELX using the prefilled syringe for the first time. Do not inject yourself or someone else until you have been shown how to inject BIMZELX the right way. Call your healthcare provider if you have any questions.
- The BIMZELX prefilled syringe has a needle safety feature that will be activated to cover the needle after the injection is finished. The needle safety feature will help to prevent needle stick injuries to anyone who handles the prefilled syringe after injection.
- Do notshare or reuse your BIMZELX prefilled syringe. You may give or get an infection.
- Do notremove the needle cap until just before you give the injection.

How should I store BIMZELX prefilled syringe?

- Store the BIMZELX prefilled syringe in the refrigerator between 36°F to 46°F (2°C to 8°C).
- BIMZELX prefilled syringes may be stored at room temperature up to 77°F (25°C) in the original carton for up to 30 days. Do not place BIMZELX prefilled syringes back in the refrigerator after they have been stored at room temperature.
- Write the date removed from the refrigerator in the space provided on the carton and throw away if it has been kept at room temperature and not used within 30 days.
- Keep the BIMZELX prefilled syringe in the original carton until ready for use to protect from light.
- Do not freeze BIMZELX.
- Do not shake BIMZELX.
- Do not use the BIMZELX prefilled syringe past the expiration date printed on the carton.

Keep BIMZELX prefilled syringes and all medicines out of the reach of children.

BIMZELX prefilled syringe parts (see Figure A):

Supplies Needed For each BIMZELX injection:

- 1 BIMZELX prefilled syringe. You may need 2 BIMZELX prefilled syringes to give the prescribed dose.

Not provided in the BIMZELX prefilled syringe carton:

- 1 alcohol swab
- 1 clean cotton ball
- 1 sharps disposal container. See, " Step 12: Dispose of (throw away) the used BIMZELX prefilled syringe" at the end of this Instructions for Use.

Setting up for your BIMZELX injection.

Step 1: Take the BIMZELX prefilled syringe carton out of the refrigerator. Do notuse the BIMZELX prefilled syringe(s) if the carton seal is broken. Throw it away and get a new one.

- Keep the BIMZELX prefilled syringe in its original carton for 30 to 45 minutesto warm to room temperature. This will help to reduce discomfort when injecting.
  - Do notmicrowave the prefilled syringe, run hot water over it, or leave it in direct sunlight
  - Do notshake the prefilled syringe.
  - Do nottake the cap off the prefilled syringe until you are ready to inject.

Step 2:Find a clean, flat, and well-lit work surface, like a table.

Step 3:Gather the supplies for your injection.

Step 4:Wash your hands well with soap and water and dry with a clean towel.

Step 5:Inspect the BIMZELX prefilled syringe (see Figure B):

- Remove the BIMZELX prefilled syringe from the carton.
- Make sure the name BIMZELX appears on the label.
  - Check the expiration date printed on the label.
  - Check the medicine through the viewing window. The medicine inside should be clear to slightly pearly, and colorless to pale brownish-yellow. You may see air bubble(s) in the liquid. This is normal.
- Do not use the BIMZELX prefilled syringe, throw it away and get a new one if:
  - The expiration date printed on the label has passed
  - The medicine is cloudy, discolored, or has particles
  - It looks damaged or has been dropped

Choose and prepare your injection site.

Step 6: Choose and clean your injection site.

- The sites you may choose for your injection are:
  - your stomach area (abdomen) or in your thigh (see Figure C).
  - the back of your arm (see Figure D) . BIMZELX may be injected into the back of your arm by a healthcare provider or caregiver only.
- Do notinject into areas where the skin is tender, bruised, red, hard, thick, scaly, or affected by psoriasis, or within 2 inches of the belly button (navel).
- Choose a new injection site on the body each time you use BIMZELX. Do notuse the same injection site 2 times in a row.

Step 7: Prepare your skin.

- Clean the injection site with an alcohol swab. Let the area dry completely. Do nottouch the cleaned area again before injecting.

Injecting BIMZELX.

Step 8: Remove the BIMZELX prefilled syringe needle cap.

- Hold the BIMZELX prefilled syringe around the finger grip with one hand. Pull the cap straight off (away from) the BIMZELX prefilled syringe with the other hand (see Figure E). You may see a drop of liquid on the tip of the needle, this is normal.
  - Putthe cap into an FDA-cleared sharps disposal container right away. You will not need it again.
  - Do nottouch the needle or let the needle touch any surface.
  - Do nothold the plunger rod during cap removal. If you accidentally remove the plunger rod, throw the BIMZELX prefilled syringe away and call your healthcare provider.
  - Do notput the needle cap back on.

Step 9:Gently pinch and hold a fold of skin where you cleaned the injection site with one hand. With the other hand, insert the needle into your skin at about a 45-degree angle.

- Push the needle all the way in to make sure that you inject your full dose. Then gently let go of your skin. Make sure the needle is in place (see Figure F).

Step 10:Firmly push the plunger head all the way down until all the medicine is injected. (see Figure G) .

- All the medicine is injected when you cannot push the plunger head any further (see Figure H).

Step 11:Lift your thumb off the plunger head (see Figure I). The needle will automatically move back in and lock in place.

- Press a clean cotton ball or gauze pad over the injection site for a few seconds. Do not rub the injection site. You may see slight bleeding or a drop of liquid. This is normal. You may cover the injection site with a small adhesive bandage, if needed.

Step 12: Dispose of (throw away) the used BIMZELX prefilled syringe (see Figure J).

- Put the used BIMZELX prefilled syringe in an FDA-cleared sharps disposal container right away after use. Do notthrow away (dispose of) the BIMZELX prefilled syringe in your household trash. If you do not have an FDA-cleared sharps disposal container, you may use a household container that is:
  - made of a heavy-duty plastic,
  - can be closed with a tight-fitting, puncture-resistant lid, without sharps being able to come out,
  - upright and stable during use,
  - leak-resistant, and
  - properly labeled to warn of hazardous waste inside the container.
- When your sharps disposal container is almost full, you will need to follow your community guidelines for the right way to dispose of your sharps disposal container. There may be state or local laws about how you should throw away needles and syringes. For more information about safe sharps disposal, and for specific information about sharps disposal in the state you live in, go to the FDA's website at: http://www.fda.gov/safesharpsdisposal.
- Do notrecycle your used sharps disposal container.

Step 13: Repeat steps 1 through 12 with a new BIMZELX prefilled syringe if you need to use 2 prefilled syringes to give the prescribed dose.

- Make sure to select a new injection site on the body each time you use BIMZELX. Do notuse the same site that you used for your first injection.

You can sign up to receive sharps containers for BIMZELX syringe disposal at no additional cost by going to www.BIMZELX.com or call 1-844-599-2273.

Manufactured by:
UCB, Inc.
1950 Lake Park Drive Smyrna, GA 30080
US License No. 1736

This Instructions for Use has been approved by the U.S. Food and Drug Administration.

Issued: 9/2024

INSTRUCTIONS for USE BIMZELX®(bim zel' ex) (bimekizumab-bkzx) injection, for subcutaneous use 320 mg/2 mL single-dose autoinjector

This Instructions for Use contains information on how to inject BIMZELX.

Read this Instructions for Use before using the BIMZELX autoinjector and each time you get a refill. There may be new information. This information does not take the place of talking to your healthcare provider about your medical condition or treatment.

Each BIMZELX autoinjector is for one-time (single-dose) use only.

Important Information you Need to Know Before Injecting BIMZELX:

- Your healthcare provider should show you or a caregiver how to prepare and inject BIMZELX using the autoinjector for the first time. Do not inject yourself or someone else until you have been shown how to inject BIMZELX the right way. Call your healthcare provider if you have any questions.
- These instructions are for 1 injection only.
- The BIMZELX autoinjector has a needle safety feature that will be activated to cover the needle after the injection is finished. The needle safety feature will help to prevent needle stick injuries to anyone who handles the autoinjector after injection.
- Do notshare or reuse your BIMZELX autoinjector. You may give or get an infection.
- Do notremove the needle cap until just before you give the injection.
- If you have vision or hearing problems, do notuse the BIMZELX autoinjector without help from a caregiver.

How should I store BIMZELX autoinjector?

- Store the BIMZELX autoinjector in the refrigerator between 36°F to 46°F (2°C to 8°C).
- BIMZELX autoinjectors may be stored at room temperature up to 77°F (25°C) in the original carton for up to 30 days. Do notplace BIMZELX autoinjectors back in the refrigerator after they have been stored at room temperature.
- Write the date removed from the refrigerator in the space provided on the carton and throw away if it has been kept at room temperature and not used within 30 days.
- Keep BIMZELX in the original carton until ready for use to protect from light.
- Do not freeze BIMZELX.
- Do not shake BIMZELX.
- Do not use the BIMZELX autoinjector past the expiration date printed on the carton.

Keep BIMZELX autoinjectors and all medicines out of the reach of children.

BIMZELX autoinjector parts (see Figure A):

Supplies Needed for each BIMZELX injection

- 1 BIMZELX autoinjector

Not provided in the BIMZELX autoinjector carton:

- 1 alcohol swab
- 1 clean cotton ball
- 1 sharps disposal container. See, " Step 12: Dispose of (throw away) the used BIMZELX autoinjector" at the end of this Instructions for Use.

Setting up for your BIMZELX injection.

Step 1: Take the BIMZELX autoinjector carton out of the refrigerator. Do notuse the BIMZELX autoinjector(s) if the carton seal is broken. Throw it away and get a new one.

- Keep the BIMZELX autoinjector in its original carton for 30 to 45 minutesto warm to room temperature. This will help to reduce discomfort when injecting.
  - Do notmicrowave the autoinjector, run hot water over it, or leave it in direct sunlight.
  - Do notshake the autoinjector.
  - Do nottake the cap off the autoinjector until you are ready to inject.

Step 2: Find a clean, flat, and well-lit work surface, like a table.

Step 3:Gather the supplies needed for your injection.

Step 4:Wash your hands well with soap and water and dry with a clean towel.

Step 5:Inspect the BIMZELX autoinjector (see Figure B):

- Remove the BIMZELX autoinjector from the carton.
- Make sure the name BIMZELX appears on the label.
  - Check the expiration date printed on the label.
  - Check the medicine through the Viewing Window. The medicine inside should be clear to slightly pearly, and colorless to pale brownish-yellow. You may see air bubble(s) in the liquid. This is normal.
- Do not use the BIMZELX autoinjector,throw it away and get a new one if:
  - The expiration date printed on the label has passed.
  - The medicine is cloudy, discolored, or has particles.
  - It looks damaged or has been dropped.

Choose and prepare your injection site.

Step 6: Choose and clean your injection site.

- The sites you may choose for your injection are:
  - your stomach area (abdomen) or your thigh (see Figure C).
  - the back of your arm (see Figure D). BIMZELX may be injected into the back of your arm by a healthcare provider or caregiver only.

- Do notinject into areas where the skin is tender, bruised, red, hard, thick, scaly, or affected by psoriasis, or within 2 inches of the belly button (navel).
- You should change (rotate) your injection site with each injection. Do notuse the same injection site 2 times in a row.

Step 7: Prepare your skin

- Clean the injection site with an alcohol swab. Let the area dry completely. Do nottouch the cleaned area again before injecting.

Injecting BIMZELX.

Step 8: Remove the BIMZELX autoinjector cap.

- Hold the BIMZELX autoinjector firmly with one hand around the handle. Pull the cap straight off (away from) the autoinjector with the other hand (see Figure E). Although you cannot see the needle tip, it is now uncovered.
  - Putthe cap into an FDA-cleared sharps disposal container right away. You will not need it again.
  - Do nottouch the needle guard or put the cap back on as it could activate the autoinjector and you can stick yourself.

Step 9:Hold the BIMZELX autoinjector at a 90-degree angle to the cleaned injection site (see Figure F).

Step 10:Place the BIMZELX autoinjector flat against your skin, then firmly press the BIMZELX autoinjector down against your skin

You will hear a "click" sound. Your injection begins when the 1st"click" is heard (see Figure G) .; - Do notlift the autoinjector away from the skin.; Keep holding the BIMZELX autoinjector in place and pressed firmly against your skin. It will take about 20 seconds to receive your full dose. |  | - You will hear a 2nd"click" that tells you the injection is almost complete. You should see the yellow color indicator filling the viewing window (see Figure H) . |  | - After the 2nd click, continue to hold down the BIMZELX autoinjector for an additional 5 seconds (slowly count to 5). This will ensure you receive your full dose (see Figure I).
You will hear a "click" sound. Your injection begins when the 1st"click" is heard (see Figure G) .; - Do notlift the autoinjector away from the skin.; Keep holding the BIMZELX autoinjector in place and pressed firmly against your skin. It will take about 20 seconds to receive your full dose. |  |  |  | - After the 2nd click, continue to hold down the BIMZELX autoinjector for an additional 5 seconds (slowly count to 5). This will ensure you receive your full dose (see Figure I).
You will hear a "click" sound. Your injection begins when the 1st"click" is heard (see Figure G) .; - Do notlift the autoinjector away from the skin.; Keep holding the BIMZELX autoinjector in place and pressed firmly against your skin. It will take about 20 seconds to receive your full dose.

Important: When you remove the autoinjector, if the window has not turned yellow this means you may not have received a full dose. Call your healthcare provider right away.

Step 11:Remove the BIMZELX autoinjector by carefully pulling the BIMZELX autoinjector straight up from your skin. The needle guard will automatically cover the needle. Do nottry to touch the needle.

- Press a clean cotton ball over the injection site for a few seconds. Do notrub the injection site. You may see slight bleeding or a drop of liquid. This is normal. You may cover the injection site with a small adhesive bandage, if needed.

Step 12: Dispose of (throw away) the used BIMZELX autoinjector (see Figure I).

- Put the used BIMZELX autoinjector in an FDA-cleared sharps disposal container right away after use. Do notthrow away (dispose of) the BIMZELX autoinjector in your household trash. If you do not have an FDA-cleared sharps disposal container, you may use a household container that is:
  - made of a heavy-duty plastic,
  - can be closed with a tight-fitting, puncture-resistant lid, without sharps being able to come out,
  - upright and stable during use,
  - leak-resistant, and
  - properly labeled to warn of hazardous waste inside the container.
- When your sharps disposal container is almost full, you will need to follow your community guidelines for the right way to dispose of your sharps disposal container. There may be state or local laws about how you should throw away needles and syringes. For more information about safe sharps disposal, and for specific information about sharps disposal in the state you live in, go to the FDA's website at:
  http://www.fda.gov/safesharpsdisposal.
- Do notrecycle your used sharps disposal container.

You can sign up to receive sharps containers for BIMZELX autoinjector disposal at no additional cost by going to www.BIMZELX.comor call 1-844-599-2273.

Manufactured by:
UCB, Inc. 1950 Lake Park Drive Smyrna, GA 30080
US License No. 1736

This Instructions for Use has been approved by the U.S. Food and Drug Administration.

Revised: 10/2024

INSTRUCTIONS for USE BIMZELX®(bim zel' ex) (bimekizumab-bkzx) injection, for subcutaneous use 320 mg/ 2 mL single-dose prefilled syringe

This Instructions for Use contains information on how to inject BIMZELX.

Read this Instructions for Use before using the BIMZELX prefilled syringe and each time you get a refill. There may be new information. This information does not take the place of talking to your healthcare provider about your medical condition or treatment.

Each BIMZELX prefilled syringe is for one-time (single-dose) use only.

Important Information you Need to Know Before Injecting BIMZELX:

- Your healthcare provider should show you or a caregiver how to prepare and inject BIMZELX using the prefilled syringe for the first time. Do not inject yourself or someone else until you have been shown how to inject BIMZELX the right way. Call your healthcare provider if you have any questions.
- These instructions are for 1 injection only.
- The BIMZELX prefilled syringe has a needle safety feature that will be activated to cover the needle after the injection is finished. The needle safety feature will help to prevent needle stick injuries to anyone who handles the prefilled syringe after injection.
- Do notshare or reuse your BIMZELX prefilled syringe. You may give or get an infection.
- Do notremove the needle cap until just before you give the injection.

How should I store BIMZELX prefilled syringe?

- Store the BIMZELX prefilled syringe in the refrigerator between 36°F to 46°F (2°C to 8°C).
- BIMZELX prefilled syringes may be stored at room temperature up to 77°F (25°C) in the original carton for up to 30 days. Do not place BIMZELX prefilled syringes back in the refrigerator after they have been stored at room temperature.
- Write the date removed from the refrigerator in the space provided on the carton and throw away if it has been kept at room temperature and not used within 30 days.
- Keep the BIMZELX prefilled syringe in the original carton until ready for use to protect from light.
- Do not freeze BIMZELX.
- Do not shake BIMZELX.
- Do not use the BIMZELX prefilled syringe past the expiration date printed on the carton.

Keep BIMZELX prefilled syringes and all medicines out of the reach of children.

BIMZELX prefilled syringe parts (see Figure A):

Supplies Needed For each BIMZELX injection:

- 1 BIMZELX prefilled syringe

Not provided in the BIMZELX prefilled syringe carton:

- 1 alcohol swab
- 1 clean cotton ball
- 1 sharps disposal container. See, " Step 12: Dispose of (throw away) the used BIMZELX prefilled syringe" at the end of this Instructions for Use.

Setting up for your BIMZELX injection.

Step 1: Take the BIMZELX prefilled syringe carton out of the refrigerator. Do notuse the BIMZELX prefilled syringe(s) if the carton seal is broken. Throw it away and get a new one.

- Keep the BIMZELX prefilled syringe in its original carton for 30 to 45 minutesto warm to room temperature. This will help to reduce discomfort when injecting.
  - Do notmicrowave the prefilled syringe, run hot water over it, or leave it in direct sunlight
  - Do notshake the prefilled syringe.
  - Do nottake the cap off the prefilled syringe until you are ready to inject.

Step 2:Find a clean, flat, and well-lit work surface, like a table.

Step 3:Gather the supplies for your injection.

Step 4:Wash your hands well with soap and water and dry with a clean towel.

Step 5:Inspect the BIMZELX prefilled syringe (see Figure B):

- Remove the BIMZELX prefilled syringe from the carton.
- Make sure the name BIMZELX appears on the label.
  - Check the expiration date printed on the label.
  - Check the medicine through the viewing window. The medicine inside should be clear to slightly pearly, and colorless to pale brownish-yellow. You may see air bubble(s) in the liquid. This is normal.
- Do not use the BIMZELX prefilled syringe, throw it away and get a new one if:
  - The expiration date printed on the label has passed
  - The medicine is cloudy, discolored, or has particles
  - It looks damaged or has been dropped

Choose and prepare your injection site.

Step 6: Choose and clean your injection site.

- The sites you may choose for your injection are:
  - your stomach area (abdomen) or in your thigh (see Figure C).
  - the back of your arm (see Figure D) . BIMZELX may be injected into the back of your arm by a healthcare provider or caregiver only.

- Do notinject into areas where the skin is tender, bruised, red, hard, thick, scaly, or affected by psoriasis, or within 2 inches of the belly button (navel).
- You should change (rotate) your injection site with each injection. Do notuse the same injection site 2 times in a row.

Step 7: Prepare your skin.

- Clean the injection site with an alcohol swab. Let the area dry completely. Do nottouch the cleaned area again before injecting.

Injecting BIMZELX.

Step 8: Remove the BIMZELX prefilled syringe needle cap.

- Hold the BIMZELX prefilled syringe around the finger grip with one hand. Pull the cap straight off (away from) the BIMZELX prefilled syringe with the other hand (see Figure E). You may see a drop of liquid on the tip of the needle, this is normal.
  - Putthe cap into an FDA-cleared sharps disposal container right away. You will not need it again.
  - Do nottouch the needle or let the needle touch any surface.
  - Do nothold the plunger rod during cap removal. If you accidentally remove the plunger rod, throw the BIMZELX prefilled syringe away and call your healthcare provider.
  - Do notput the needle cap back on.

Step 9:Gently pinch and hold a fold of skin where you cleaned the injection site with one hand. With the other hand, insert the needle into your skin at about a 45-degree angle.

- Push the needle all the way in to make sure that you inject your full dose. Then gently let go of your skin. Make sure the needle is in place (see Figure F).

Step 10:Firmly push the plunger head all the way down until all the medicine is injected. (see Figure G) .

- All the medicine is injected when you cannot push the plunger head any further (see Figure H).

Step 11:Lift your thumb off the plunger head (see Figure I). The needle will automatically move back in and lock in place.

- Press a clean cotton ball or gauze pad over the injection site for a few seconds. Do not rub the injection site. You may see slight bleeding or a drop of liquid. This is normal. You may cover the injection site with a small adhesive bandage, if needed.

Step 12: Dispose of (throw away) the used BIMZELX prefilled syringe (see Figure J).

- Put the used BIMZELX prefilled syringe in an FDA-cleared sharps disposal container right away after use. Do notthrow away (dispose of) the BIMZELX prefilled syringe in your household trash. If you do not have an FDA-cleared sharps disposal container, you may use a household container that is:
  - made of a heavy-duty plastic,
  - can be closed with a tight-fitting, puncture-resistant lid, without sharps being able to come out,
  - upright and stable during use,
  - leak-resistant, and
  - properly labeled to warn of hazardous waste inside the container.
- When your sharps disposal container is almost full, you will need to follow your community guidelines for the right way to dispose of your sharps disposal container. There may be state or local laws about how you should throw away needles and syringes. For more information about safe sharps disposal, and for specific information about sharps disposal in the state you live in, go to the FDA's website at: http://www.fda.gov/safesharpsdisposal.
- Do notrecycle your used sharps disposal container.

You can sign up to receive sharps containers for BIMZELX syringe disposal at no additional cost by going to www.BIMZELX.com or call 1-844-599-2273.

Manufactured by:
UCB, Inc.
1950 Lake Park Drive Smyrna, GA 30080

US License No. 1736

This Instructions for Use has been approved by the U.S. Food and Drug Administration.
Revised: 10/2024

PRINCIPAL DISPLAY PANEL - 160 mg/mL Autoinjector Carton

NDC 50474-781-85
Rx ONLY

ATTENTION: Dispense enclosed
Medication Guide to each patient.

Bimzelx®
(bimekizumab-bkzx) Injection

160 mg/mL per autoinjector
FOR SUBCUTANEOUS USE ONLY

Two single-dose autoinjectors.
Each autoinjector delivers 160 mg
in 1 mL of bimekizumab-bkzx.

For a 320 mg dose, two 160 mg
autoinjectors are required.

PRINCIPAL DISPLAY PANEL - 160 mg/mL Syringe Carton

NDC 50474-780-79
Rx ONLY

ATTENTION: Dispense enclosed
Medication Guide to each patient.

Bimzelx®
(bimekizumab-bkzx) Injection

160 mg/mL per syringe
FOR SUBCUTANEOUS USE ONLY

Two single-dose prefilled
syringes. Each syringe
delivers 160 mg in 1 mL
of bimekizumab-bkzx.

For a 320 mg dose, two 160 mg
prefilled syringes are required.

PRINCIPAL DISPLAY PANEL - 320 mg/2 mL autoinjector Carton

NDC 50474-782-84
Rx ONLY

ATTENTION: Dispense enclosed
Medication Guide to each patient.

Bimzelx®
(bimekizumab-bkzx) Injection

320 mg/2 mL autoinjector

FOR SUBCUTANEOUS USE ONLY

One single-dose autoinjector.
Each autoinjector delivers 320 mg
in 2 mL of bimekizumab-bkzx.

PRINCIPAL DISPLAY PANEL - 320 mg/2 mL Syringe Carton

NDC 50474-783-78
Rx ONLY

ATTENTION: Dispense enclosed
Medication Guide to each patient.

Bimzelx®
(bimekizumab-bkzx) Injection

320 mg/2 mL (160 mg/mL)
syringe

FOR SUBCUTANEOUS USE ONLY

One single-dose prefilled syringe.
Each syringe delivers 320 mg
in 2 mL of bimekizumab-bkzx.